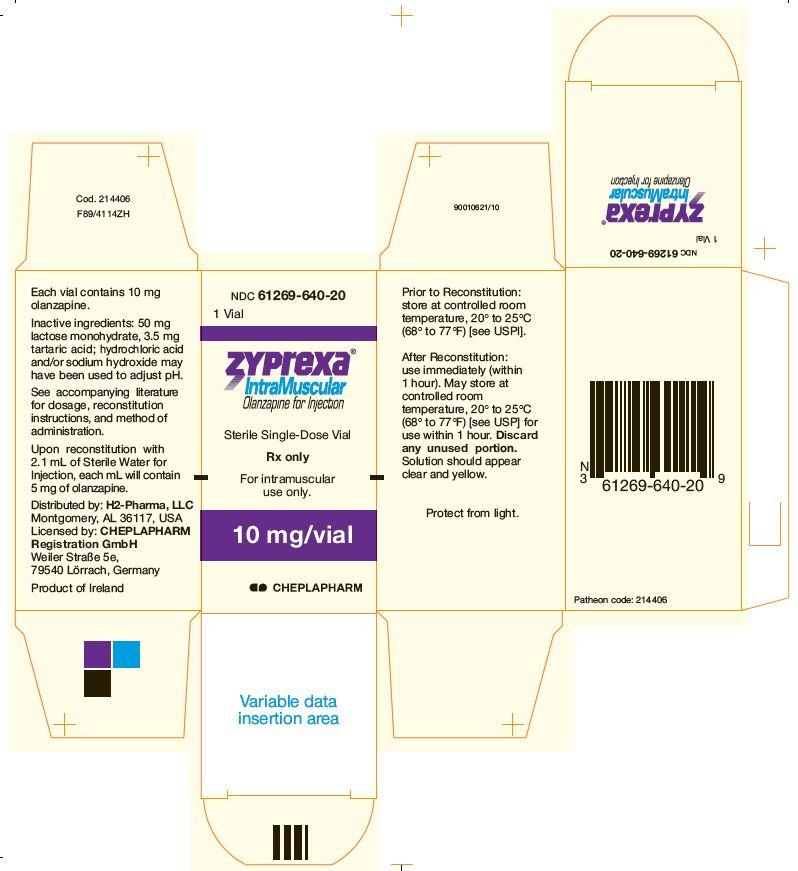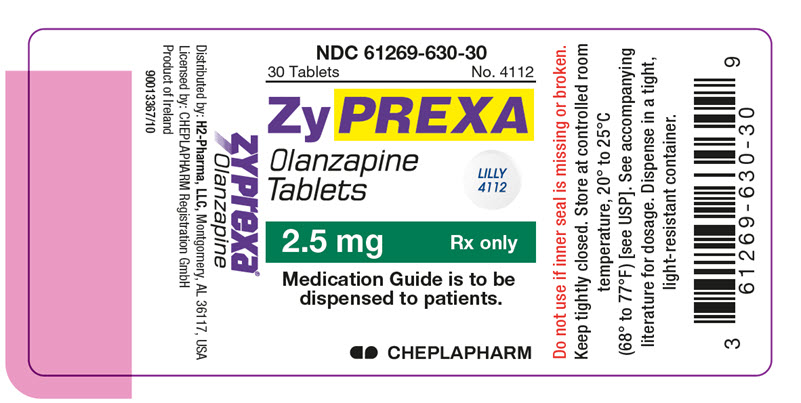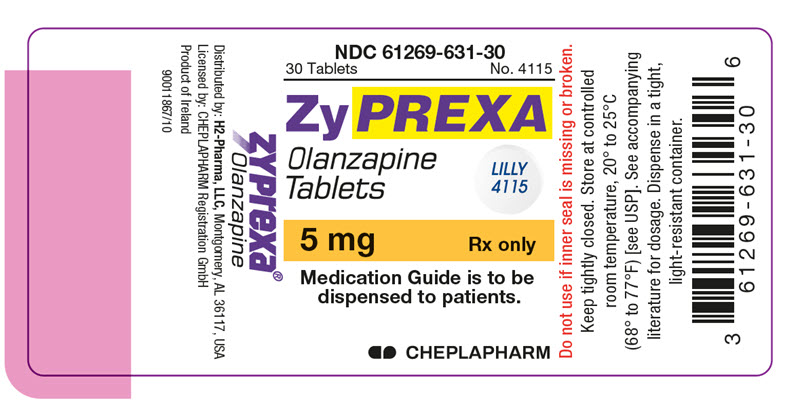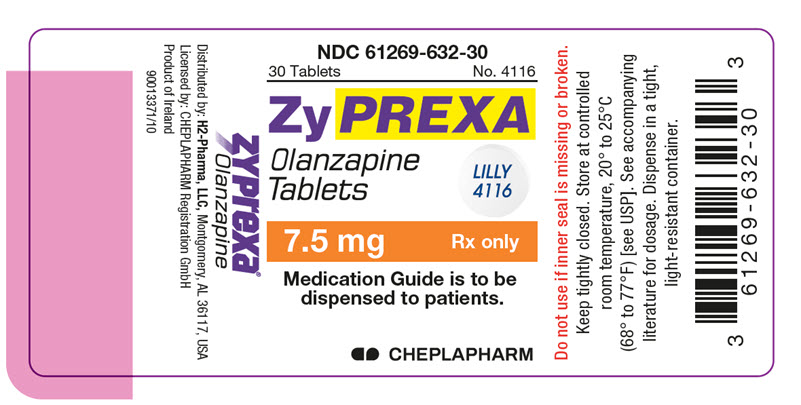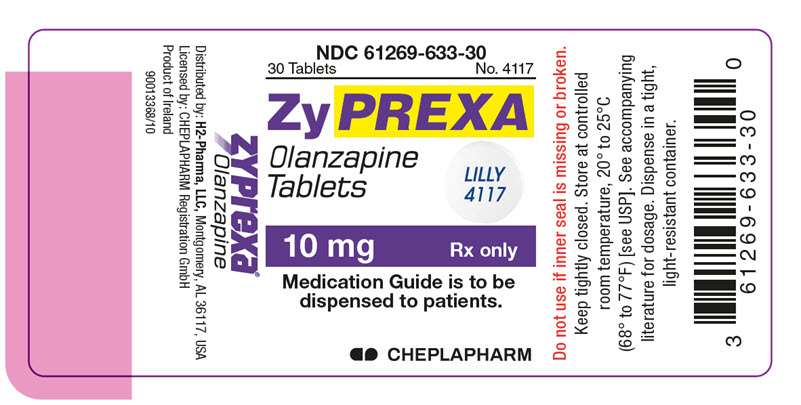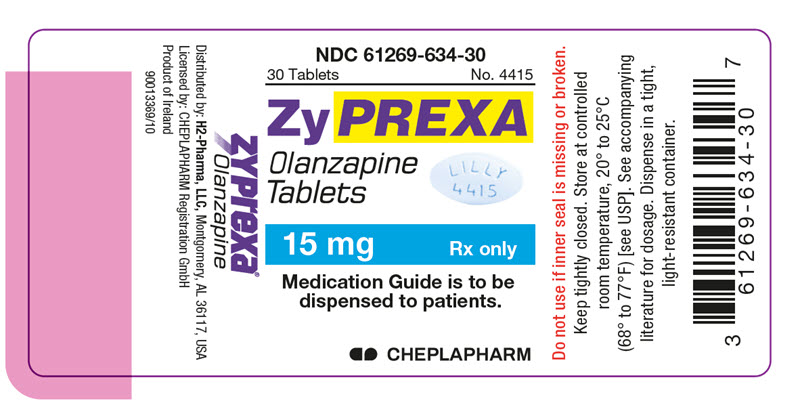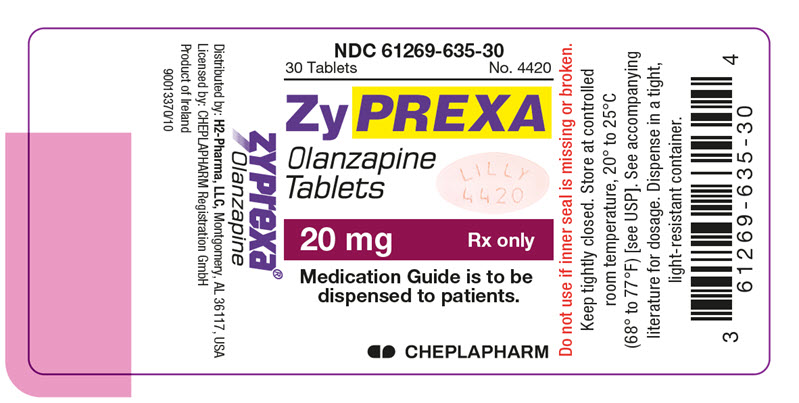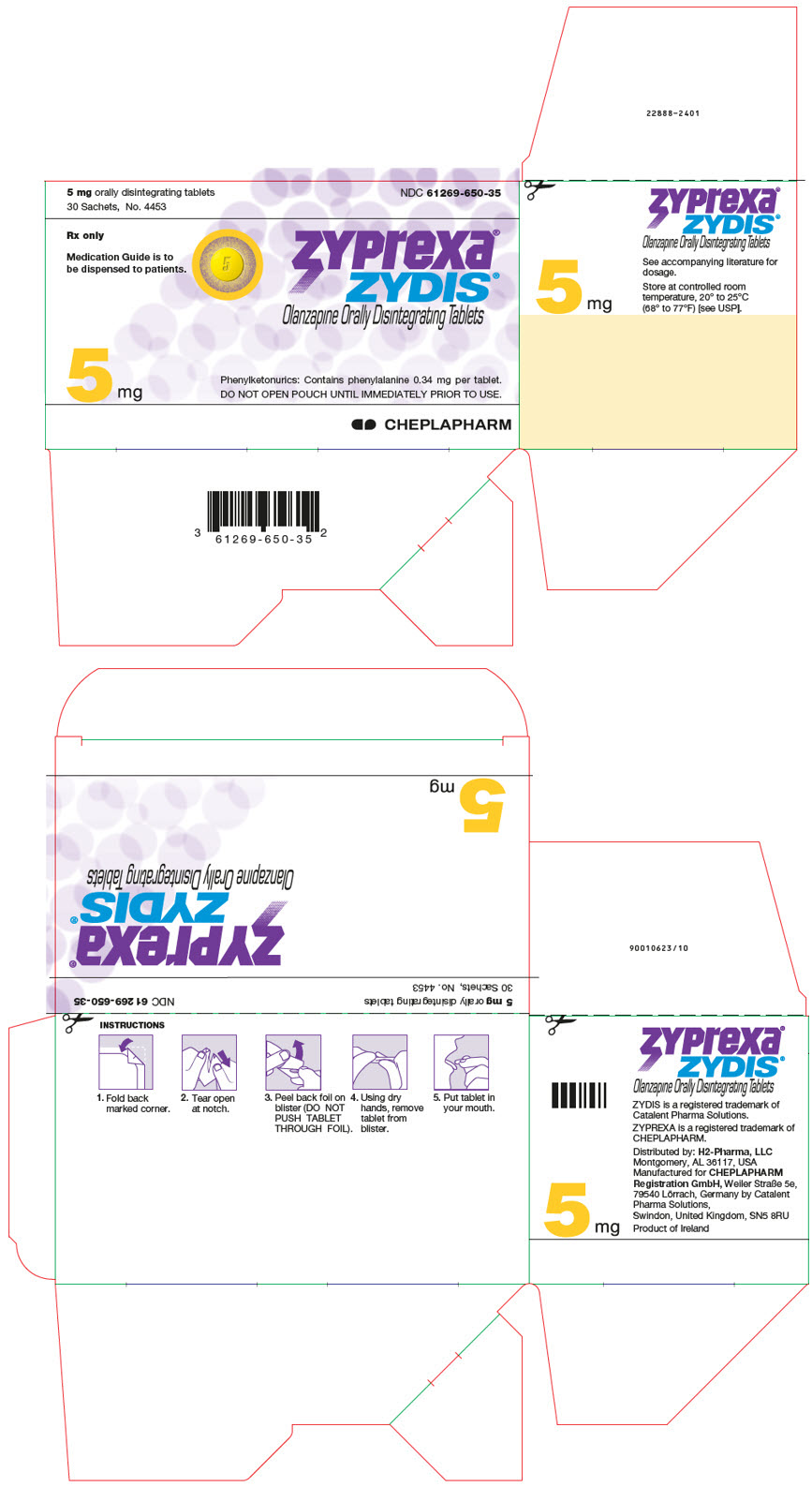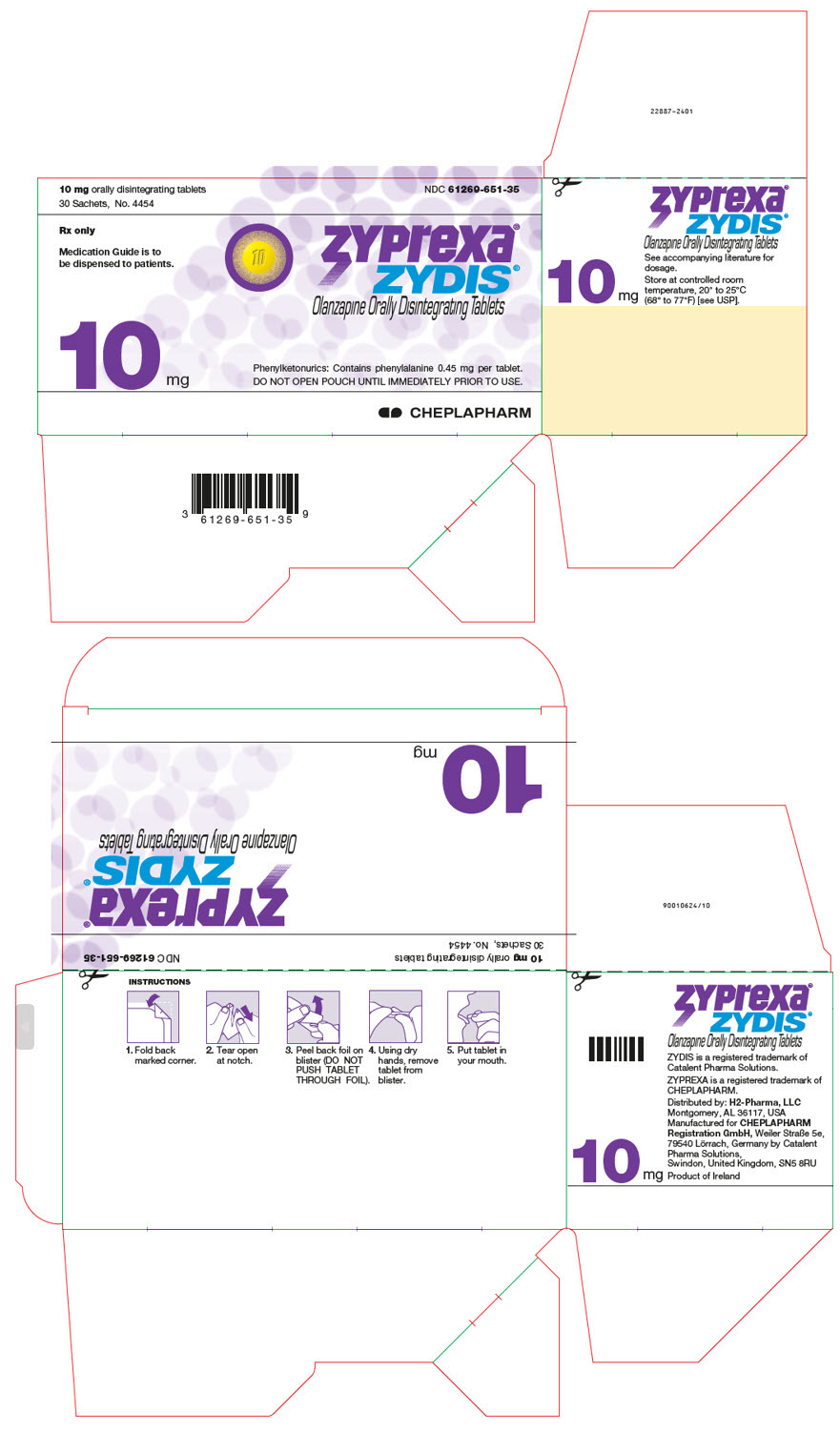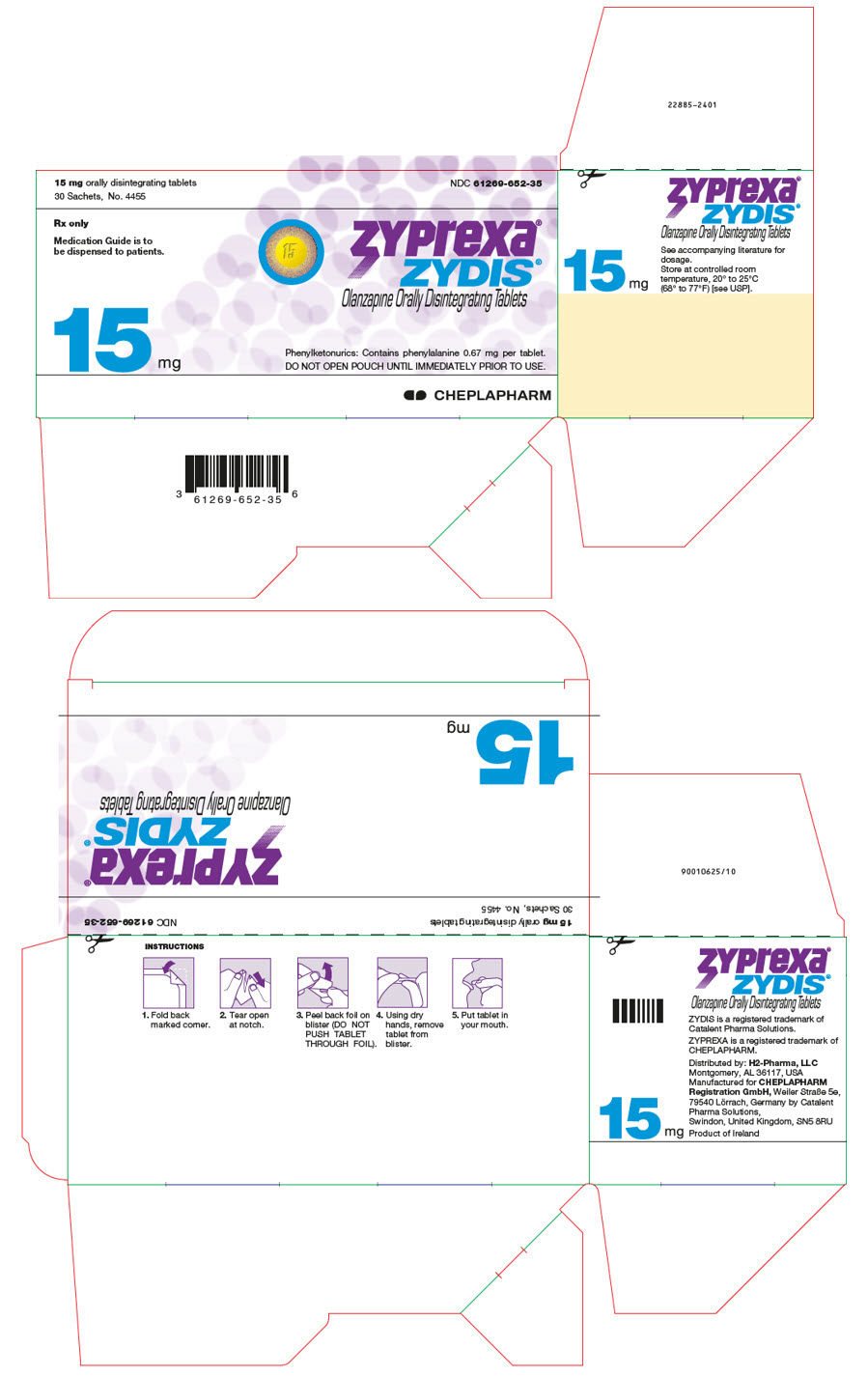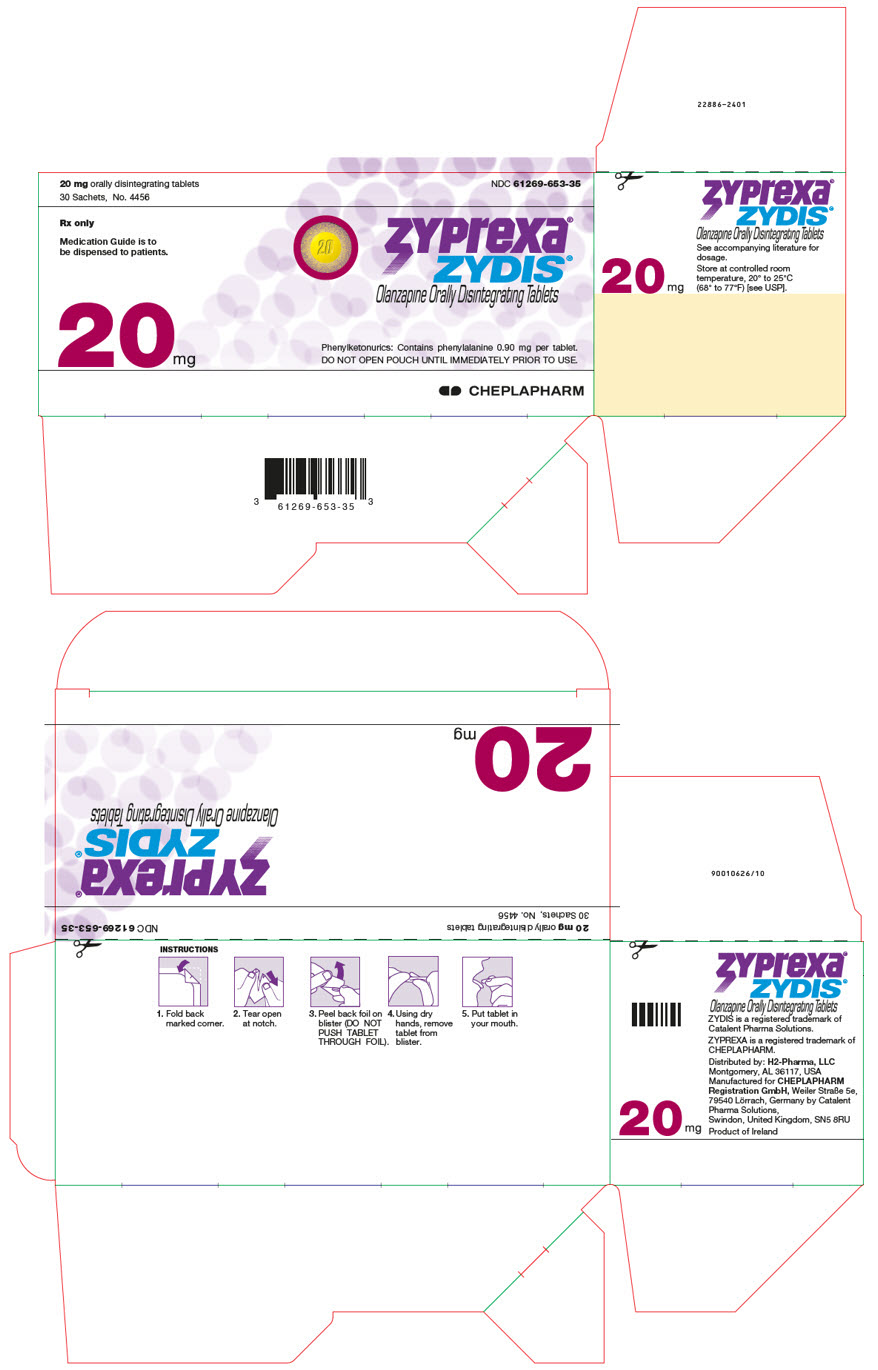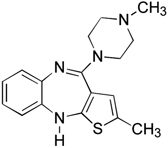 DRUG LABEL: Zyprexa
NDC: 61269-630 | Form: TABLET
Manufacturer: H2-Pharma LLC
Category: prescription | Type: HUMAN PRESCRIPTION DRUG LABEL
Date: 20260211

ACTIVE INGREDIENTS: Olanzapine 2.5 mg/1 1
INACTIVE INGREDIENTS: Carnauba wax; Crospovidone, Unspecified; Hydroxypropyl Cellulose, Unspecified; Hypromellose, Unspecified; Lactose, Unspecified Form; Magnesium stearate; Microcrystalline cellulose; Titanium dioxide; Polyethylene Glycol, Unspecified; Polysorbate 80

HIGHLIGHTS OF PRESCRIBING INFORMATION

These highlights do not include all the information needed to use ZYPREXA safely and effectively. See full prescribing information for ZYPREXA.
ZYPREXA (olanzapine) Tablet for Oral use
ZYPREXA ZYDIS (olanzapine) Tablet, Orally Disintegrating for Oral use
ZYPREXA IntraMuscular (olanzapine) Injection, Powder, For Solution for Intramuscular use
Initial U.S. Approval: 1996

RECENT MAJOR CHANGES

None

WARNING: INCREASED MORTALITY IN ELDERLY PATIENTS WITH DEMENTIA-RELATED PSYCHOSIS

See full prescribing information for complete boxed warning.

- Elderly patients with dementia-related psychosis treated with antipsychotic drugs are at an increased risk of death. ZYPREXA is not approved for the treatment of patients with dementia-related psychosis. (5.1, 8.5, 17)
- When using ZYPREXA and fluoxetine in combination, also refer to the Boxed Warning section of the package insert for Symbyax.

1 INDICATIONS AND USAGE

ZYPREXA® (olanzapine) is an atypical antipsychotic indicated:

As oral formulation for the:

- Treatment of schizophrenia. (1.1)
  - Adults: Efficacy was established in three clinical trials in patients with schizophrenia: two 6-week trials and one maintenance trial. (14.1)
  - Adolescents (ages 13-17): Efficacy was established in one 6-week trial in patients with schizophrenia (14.1). The increased potential (in adolescents compared with adults) for weight gain and dyslipidemia may lead clinicians to consider prescribing other drugs first in adolescents. (1.1)
- Acute treatment of manic or mixed episodes associated with bipolar I disorder and maintenance treatment of bipolar I disorder. (1.2)
  - Adults: Efficacy was established in three clinical trials in patients with manic or mixed episodes of bipolar I disorder: two 3- to 4-week trials and one maintenance trial. (14.2)
  - Adolescents (ages 13-17): Efficacy was established in one 3-week trial in patients with manic or mixed episodes associated with bipolar I disorder (14.2). The increased potential (in adolescents compared with adults) for weight gain and dyslipidemia may lead clinicians to consider prescribing other drugs first in adolescents. (1.2)
- Medication therapy for pediatric patients with schizophrenia or bipolar I disorder should be undertaken only after a thorough diagnostic evaluation and with careful consideration of the potential risks. (1.3)
- Adjunct to valproate or lithium in the treatment of manic or mixed episodes associated with bipolar I disorder. (1.2)
  - Efficacy was established in two 6-week clinical trials in adults (14.2). Maintenance efficacy has not been systematically evaluated.

As ZYPREXA IntraMuscular for the:

- Treatment of acute agitation associated with schizophrenia and bipolar I mania. (1.4)
  - Efficacy was established in three 1-day trials in adults. (14.3)

As ZYPREXA and Fluoxetine in Combination for the:

- Treatment of depressive episodes associated with bipolar I disorder. (1.5)
  - Efficacy was established with Symbyax (olanzapine and fluoxetine in combination); refer to the product label for Symbyax.
- Treatment of treatment resistant depression. (1.6)
  - Efficacy was established with Symbyax (olanzapine and fluoxetine in combination) in adults; refer to the product label for Symbyax.

2 DOSAGE AND ADMINISTRATION

Schizophrenia in adults (2.1) | Oral: Start at 5-10 mg once daily; Target: 10 mg/day within several days
Schizophrenia in adolescents (2.1) | Oral: Start at 2.5-5 mg once daily; Target: 10 mg/day
Bipolar I Disorder (manic or mixed episodes) in adults (2.2) | Oral: Start at 10 or 15 mg once daily
Bipolar I Disorder (manic or mixed episodes) in adolescents (2.2) | Oral: Start at 2.5-5 mg once daily; Target: 10 mg/day
Bipolar I Disorder (manic or mixed episodes) with lithium or valproate in adults (2.2) | Oral: Start at 10 mg once daily
Agitation associated with Schizophrenia and Bipolar I Mania in adults (2.4) | IM: 10 mg (5 mg or 7.5 mg when clinically warranted) Assess for orthostatic hypotension prior to subsequent dosing (max. 3 doses 2-4 hrs apart)
Depressive Episodes associated with Bipolar I Disorder in adults (2.5) | Oral in combination with fluoxetine: Start at 5 mg of oral olanzapine and 20 mg of fluoxetine once daily
Depressive Episodes associated with Bipolar I Disorder in children and adolescents (2.5) | Oral in combination with fluoxetine: Start at 2.5 mg of oral olanzapine and 20 mg of fluoxetine once daily
Treatment Resistant Depression in adults (2.6) | Oral in combination with fluoxetine: Start at 5 mg of oral olanzapine and 20 mg of fluoxetine once daily

- Lower starting dose recommended in debilitated or pharmacodynamically sensitive patients or patients with predisposition to hypotensive reactions, or with potential for slowed metabolism. (2.1)
- Olanzapine may be given without regard to meals. (2.1)

ZYPREXA and Fluoxetine in Combination:

- Dosage adjustments, if indicated, should be made with the individual components according to efficacy and tolerability. (2.5, 2.6)
- Olanzapine monotherapy is not indicated for the treatment of depressive episodes associated with bipolar I disorder or treatment resistant depression. (2.5, 2.6)
- Safety of co-administration of doses above 18 mg olanzapine with 75 mg fluoxetine has not been evaluated in adults. (2.5, 2.6)
- Safety of co-administration of doses above 12 mg olanzapine with 50 mg fluoxetine has not been evaluated in children and adolescents ages 10 to 17. (2.5)

3 DOSAGE FORMS AND STRENGTHS

- Tablets (not scored): 2.5, 5, 7.5, 10, 15, 20 mg. (3)
- Orally Disintegrating Tablets (not scored): 5, 10, 15, 20 mg. (3)
- Intramuscular Injection: 10 mg single-dose vial. (3)

4 CONTRAINDICATIONS

- None with ZYPREXA monotherapy. (4)
- When using ZYPREXA and fluoxetine in combination, also refer to the Contraindications section of the package insert for Symbyax®. (4)
- When using ZYPREXA in combination with lithium or valproate, refer to the Contraindications section of the package inserts for those products. (4)

5 WARNINGS AND PRECAUTIONS

- Elderly Patients with Dementia-Related Psychosis: Increased risk of death and increased incidence of cerebrovascular adverse events (e.g., stroke, transient ischemic attack). (5.1)
- Suicide: The possibility of a suicide attempt is inherent in schizophrenia and in bipolar I disorder, and close supervision of high-risk patients should accompany drug therapy; when using in combination with fluoxetine, also refer to the Boxed Warning and Warnings and Precautions sections of the package insert for Symbyax. (5.2)
- Neuroleptic Malignant Syndrome: Manage with immediate discontinuation and close monitoring. (5.3)
- Drug Reaction with Eosinophilia and Systemic Symptoms (DRESS): Discontinue if DRESS is suspected. (5.4)
- Metabolic Changes: Atypical antipsychotic drugs have been associated with metabolic changes including hyperglycemia, dyslipidemia, and weight gain. (5.5)
  - Hyperglycemia and Diabetes Mellitus: In some cases extreme and associated with ketoacidosis or hyperosmolar coma or death, has been reported in patients taking olanzapine. Patients taking olanzapine should be monitored for symptoms of hyperglycemia and undergo fasting blood glucose testing at the beginning of, and periodically during, treatment. (5.5)
  - Dyslipidemia: Undesirable alterations in lipids have been observed. Appropriate clinical monitoring is recommended, including fasting blood lipid testing at the beginning of, and periodically during, treatment. (5.5)
  - Weight Gain: Potential consequences of weight gain should be considered. Patients should receive regular monitoring of weight. (5.5)
- Tardive Dyskinesia: Discontinue if clinically appropriate. (5.6)
- Orthostatic Hypotension: Orthostatic hypotension associated with dizziness, tachycardia, bradycardia and, in some patients, syncope, may occur especially during initial dose titration. Use caution in patients with cardiovascular disease, cerebrovascular disease, and those conditions that could affect hemodynamic responses. (5.7)
- Leukopenia, Neutropenia, and Agranulocytosis: Has been reported with antipsychotics, including ZYPREXA. Patients with a history of a clinically significant low white blood cell count (WBC) or drug induced leukopenia/neutropenia should have their complete blood count (CBC) monitored frequently during the first few months of therapy and discontinuation of ZYPREXA should be considered at the first sign of a clinically significant decline in WBC in the absence of other causative factors. (5.9)
- Seizures: Use cautiously in patients with a history of seizures or with conditions that potentially lower the seizure threshold. (5.11)
- Potential for Cognitive and Motor Impairment: Has potential to impair judgment, thinking, and motor skills. Use caution when operating machinery. (5.12)
- Anticholinergic (antimuscarinic) Effects: Use with caution with other anticholinergic drugs and in patients with urinary retention, prostatic hypertrophy, constipation, paralytic ileus or related conditions. (5.14)
- Hyperprolactinemia: May elevate prolactin levels. (5.15)
- Use in Combination with Fluoxetine, Lithium or Valproate: Also refer to the package inserts for Symbyax, lithium, or valproate. (5.16)
- Laboratory Tests: Monitor fasting blood glucose and lipid profiles at the beginning of, and periodically during, treatment. (5.17)

6 ADVERSE REACTIONS

Most common adverse reactions (≥5% and at least twice that for placebo) associated with:

Oral Olanzapine Monotherapy:

- Schizophrenia (Adults) – postural hypotension, constipation, weight gain, dizziness, personality disorder, akathisia. (6.1)
- Schizophrenia (Adolescents) – sedation, weight increased, headache, increased appetite, dizziness, abdominal pain, pain in extremity, fatigue, dry mouth. (6.1)
- Manic or Mixed Episodes, Bipolar I Disorder (Adults) – asthenia, dry mouth, constipation, increased appetite, somnolence, dizziness, tremor. (6.1)
- Manic or Mixed Episodes, Bipolar I Disorder (Adolescents) – sedation, weight increased, increased appetite, headache, fatigue, dizziness, dry mouth, abdominal pain, pain in extremity. (6.1)

Combination of ZYPREXA and Lithium or Valproate:

- Manic or Mixed Episodes, Bipolar I Disorder (Adults) – dry mouth, weight gain, increased appetite, dizziness, back pain, constipation, speech disorder, increased salivation, amnesia, paresthesia. (6.1)

ZYPREXA and Fluoxetine in Combination: Also refer to the Adverse Reactions section of the package insert for Symbyax. (6)

ZYPREXA IntraMuscular for Injection:

- Agitation with Schizophrenia and Bipolar I Mania (Adults) – somnolence. (6.1)

To report SUSPECTED ADVERSE REACTIONS, contact the Safety Call Center at 1-866-770-9010 or FDA at 1-800-FDA-1088 or www.fda.gov/medwatch

7 DRUG INTERACTIONS

- Diazepam: May potentiate orthostatic hypotension. (7.1, 7.2)
- Alcohol: May potentiate orthostatic hypotension. (7.1)
- Carbamazepine: Increased clearance of olanzapine. (7.1)
- Fluvoxamine: May increase olanzapine levels. (7.1)
- ZYPREXA and Fluoxetine in Combination: Also refer to the Drug Interactions section of the package insert for Symbyax. (7.1)
- CNS Acting Drugs: Caution should be used when taken in combination with other centrally acting drugs and alcohol. (7.2)
- Antihypertensive Agents: Enhanced antihypertensive effect. (7.2)
- Levodopa and Dopamine Agonists: May antagonize levodopa/dopamine agonists. (7.2)
- Lorazepam (IM): Increased somnolence with IM olanzapine. (7.2)
- Other Concomitant Drug Therapy: When using olanzapine in combination with lithium or valproate, refer to the Drug Interactions sections of the package insert for those products. (7.2)

8 USE IN SPECIFIC POPULATIONS

- Pregnancy: May cause extrapyramidal and/or withdrawal symptoms in neonates with third trimester exposure. (8.1)
- Pediatric Use: Safety and effectiveness of ZYPREXA in children <13 years of age have not been established. Safety and effectiveness of ZYPREXA and fluoxetine in combination in children <10 years of age have not been established. (8.4)

FULL PRESCRIBING INFORMATION

WARNING: INCREASED MORTALITY IN ELDERLY PATIENTS WITH DEMENTIA-RELATED PSYCHOSIS

Elderly patients with dementia-related psychosis treated with antipsychotic drugs are at an increased risk of death. Analyses of seventeen placebo-controlled trials (modal duration of 10 weeks), largely in patients taking atypical antipsychotic drugs, revealed a risk of death in drug-treated patients of between 1.6 to 1.7 times the risk of death in placebo-treated patients. Over the course of a typical 10-week controlled trial, the rate of death in drug-treated patients was about 4.5%, compared to a rate of about 2.6% in the placebo group. Although the causes of death were varied, most of the deaths appeared to be either cardiovascular (e.g., heart failure, sudden death) or infectious (e.g., pneumonia) in nature. Observational studies suggest that, similar to atypical antipsychotic drugs, treatment with conventional antipsychotic drugs may increase mortality. The extent to which the findings of increased mortality in observational studies may be attributed to the antipsychotic drug as opposed to some characteristic(s) of the patients is not clear. ZYPREXA (olanzapine) is not approved for the treatment of patients with dementia-related psychosis [see Warnings and Precautions (5.1), Use in Specific Populations (8.5), and Patient Counseling Information (17)].

When using ZYPREXA and fluoxetine in combination, also refer to the Boxed Warning section of the package insert for Symbyax.

1 INDICATIONS AND USAGE

1.1 Schizophrenia

Oral ZYPREXA is indicated for the treatment of schizophrenia. Efficacy was established in three clinical trials in adult patients with schizophrenia: two 6-week trials and one maintenance trial. In adolescent patients with schizophrenia (ages 13-17), efficacy was established in one 6-week trial [see Clinical Studies (14.1)].

When deciding among the alternative treatments available for adolescents, clinicians should consider the increased potential (in adolescents as compared with adults) for weight gain and dyslipidemia. Clinicians should consider the potential long-term risks when prescribing to adolescents, and in many cases this may lead them to consider prescribing other drugs first in adolescents [see Warnings and Precautions (5.5)].

1.2 Bipolar I Disorder (Manic or Mixed Episodes)

Monotherapy — Oral ZYPREXA is indicated for the acute treatment of manic or mixed episodes associated with bipolar I disorder and maintenance treatment of bipolar I disorder. Efficacy was established in three clinical trials in adult patients with manic or mixed episodes of bipolar I disorder: two 3- to 4-week trials and one monotherapy maintenance trial. In adolescent patients with manic or mixed episodes associated with bipolar I disorder (ages 13-17), efficacy was established in one 3-week trial [see Clinical Studies (14.2)].

When deciding among the alternative treatments available for adolescents, clinicians should consider the increased potential (in adolescents as compared with adults) for weight gain and dyslipidemia. Clinicians should consider the potential long-term risks when prescribing to adolescents, and in many cases this may lead them to consider prescribing other drugs first in adolescents [see Warnings and Precautions (5.5)].

Adjunctive Therapy to Lithium or Valproate — Oral ZYPREXA is indicated for the treatment of manic or mixed episodes associated with bipolar I disorder as an adjunct to lithium or valproate. Efficacy was established in two 6-week clinical trials in adults. The effectiveness of adjunctive therapy for longer-term use has not been systematically evaluated in controlled trials [see Clinical Studies (14.2)].

1.3 Special Considerations in Treating Pediatric Schizophrenia and Bipolar I Disorder

Pediatric schizophrenia and bipolar I disorder are serious mental disorders; however, diagnosis can be challenging. For pediatric schizophrenia, symptom profiles can be variable, and for bipolar I disorder, pediatric patients may have variable patterns of periodicity of manic or mixed symptoms. It is recommended that medication therapy for pediatric schizophrenia and bipolar I disorder be initiated only after a thorough diagnostic evaluation has been performed and careful consideration given to the risks associated with medication treatment. Medication treatment for both pediatric schizophrenia and bipolar I disorder should be part of a total treatment program that often includes psychological, educational and social interventions.

1.4 ZYPREXA IntraMuscular: Agitation Associated with Schizophrenia and Bipolar I Mania

ZYPREXA IntraMuscular is indicated for the treatment of acute agitation associated with schizophrenia and bipolar I mania.

Efficacy was demonstrated in 3 short-term (24 hours of IM treatment) placebo-controlled trials in agitated adult inpatients with: schizophrenia or bipolar I disorder (manic or mixed episodes) [see Clinical Studies (14.3)].

"Psychomotor agitation" is defined in DSM-IV as "excessive motor activity associated with a feeling of inner tension." Patients experiencing agitation often manifest behaviors that interfere with their diagnosis and care, e.g., threatening behaviors, escalating or urgently distressing behavior, or self-exhausting behavior, leading clinicians to the use of intramuscular antipsychotic medications to achieve immediate control of the agitation.

1.5 ZYPREXA and Fluoxetine in Combination: Depressive Episodes Associated with Bipolar I Disorder

Oral ZYPREXA and fluoxetine in combination is indicated for the treatment of depressive episodes associated with bipolar I disorder, based on clinical studies. When using ZYPREXA and fluoxetine in combination, refer to the Clinical Studies section of the package insert for Symbyax.

ZYPREXA monotherapy is not indicated for the treatment of depressive episodes associated with bipolar I disorder.

1.6 ZYPREXA and Fluoxetine in Combination: Treatment Resistant Depression

Oral ZYPREXA and fluoxetine in combination is indicated for the treatment of treatment resistant depression (major depressive disorder in patients who do not respond to 2 separate trials of different antidepressants of adequate dose and duration in the current episode), based on clinical studies in adult patients. When using ZYPREXA and fluoxetine in combination, refer to the Clinical Studies section of the package insert for Symbyax.

ZYPREXA monotherapy is not indicated for the treatment of treatment resistant depression.

2 DOSAGE AND ADMINISTRATION

2.1 Schizophrenia

Adults

Dose Selection — Oral olanzapine should be administered on a once-a-day schedule without regard to meals, generally beginning with 5 to 10 mg initially, with a target dose of 10 mg/day within several days. Further dosage adjustments, if indicated, should generally occur at intervals of not less than 1 week, since steady state for olanzapine would not be achieved for approximately 1 week in the typical patient. When dosage adjustments are necessary, dose increments/decrements of 5 mg QD are recommended.

Efficacy in schizophrenia was demonstrated in a dose range of 10 to 15 mg/day in clinical trials. However, doses above 10 mg/day were not demonstrated to be more efficacious than the 10 mg/day dose. An increase to a dose greater than the target dose of 10 mg/day (i.e., to a dose of 15 mg/day or greater) is recommended only after clinical assessment. Olanzapine is not indicated for use in doses above 20 mg/day.

Dosing in Special Populations — The recommended starting dose is 5 mg in patients who are debilitated, who have a predisposition to hypotensive reactions, who otherwise exhibit a combination of factors that may result in slower metabolism of olanzapine (e.g., nonsmoking female patients ≥65 years of age), or who may be more pharmacodynamically sensitive to olanzapine [see Warnings and Precautions (5.14), Drug Interactions (7), and Clinical Pharmacology (12.3)]. When indicated, dose escalation should be performed with caution in these patients.

Maintenance Treatment — The effectiveness of oral olanzapine, 10 mg/day to 20 mg/day, in maintaining treatment response in schizophrenic patients who had been stable on ZYPREXA for approximately 8 weeks and were then followed for relapse has been demonstrated in a placebo-controlled trial [see Clinical Studies (14.1)]. The healthcare provider who elects to use ZYPREXA for extended periods should periodically reevaluate the long-term usefulness of the drug for the individual patient.

Adolescents

Dose Selection — Oral olanzapine should be administered on a once-a-day schedule without regard to meals with a recommended starting dose of 2.5 or 5 mg, with a target dose of 10 mg/day. Efficacy in adolescents with schizophrenia was demonstrated based on a flexible dose range of 2.5 to 20 mg/day in clinical trials, with a mean modal dose of 12.5 mg/day (mean dose of 11.1 mg/day). When dosage adjustments are necessary, dose increments/decrements of 2.5 or 5 mg are recommended.

The safety and effectiveness of doses above 20 mg/day have not been evaluated in clinical trials [see Clinical Studies (14.1)].

Maintenance Treatment — The efficacy of ZYPREXA for the maintenance treatment of schizophrenia in the adolescent population has not been systematically evaluated; however, maintenance efficacy can be extrapolated from adult data along with comparisons of olanzapine pharmacokinetic parameters in adult and adolescent patients. Thus, it is generally recommended that responding patients be continued beyond the acute response, but at the lowest dose needed to maintain remission. Patients should be periodically reassessed to determine the need for maintenance treatment.

2.2 Bipolar I Disorder (Manic or Mixed Episodes)

Adults

Dose Selection for Monotherapy — Oral olanzapine should be administered on a once-a-day schedule without regard to meals, generally beginning with 10 or 15 mg. Dosage adjustments, if indicated, should generally occur at intervals of not less than 24 hours, reflecting the procedures in the placebo-controlled trials. When dosage adjustments are necessary, dose increments/decrements of 5 mg QD are recommended.

Short-term (3-4 weeks) antimanic efficacy was demonstrated in a dose range of 5 mg to 20 mg/day in clinical trials. The safety of doses above 20 mg/day has not been evaluated in clinical trials [see Clinical Studies (14.2)].

Maintenance Monotherapy — The benefit of maintaining bipolar I patients on monotherapy with oral ZYPREXA at a dose of 5 to 20 mg/day, after achieving a responder status for an average duration of 2 weeks, was demonstrated in a controlled trial [see Clinical Studies (14.2)]. The healthcare provider who elects to use ZYPREXA for extended periods should periodically reevaluate the long-term usefulness of the drug for the individual patient.

Dose Selection for Adjunctive Treatment — When administered as adjunctive treatment to lithium or valproate, oral olanzapine dosing should generally begin with 10 mg once-a-day without regard to meals.

Antimanic efficacy was demonstrated in a dose range of 5 mg to 20 mg/day in clinical trials [see Clinical Studies (14.2)]. The safety of doses above 20 mg/day has not been evaluated in clinical trials.

Adolescents

Dose Selection — Oral olanzapine should be administered on a once-a-day schedule without regard to meals with a recommended starting dose of 2.5 or 5 mg, with a target dose of 10 mg/day. Efficacy in adolescents with bipolar I disorder (manic or mixed episodes) was demonstrated based on a flexible dose range of 2.5 to 20 mg/day in clinical trials, with a mean modal dose of 10.7 mg/day (mean dose of 8.9 mg/day). When dosage adjustments are necessary, dose increments/decrements of 2.5 or 5 mg are recommended.

The safety and effectiveness of doses above 20 mg/day have not been evaluated in clinical trials [see Clinical Studies (14.2)].

Maintenance Treatment — The efficacy of ZYPREXA for the maintenance treatment of bipolar I disorder in the adolescent population has not been evaluated; however, maintenance efficacy can be extrapolated from adult data along with comparisons of olanzapine pharmacokinetic parameters in adult and adolescent patients. Thus, it is generally recommended that responding patients be continued beyond the acute response, but at the lowest dose needed to maintain remission. Patients should be periodically reassessed to determine the need for maintenance treatment.

2.3 Administration of ZYPREXA ZYDIS (olanzapine orally disintegrating tablets)

After opening sachet, peel back foil on blister. Do not push tablet through foil. Immediately upon opening the blister, using dry hands, remove tablet and place entire ZYPREXA ZYDIS in the mouth. Tablet disintegration occurs rapidly in saliva so it can be easily swallowed with or without liquid.

2.4 ZYPREXA IntraMuscular: Agitation Associated with Schizophrenia and Bipolar I Mania

Dose Selection for Agitated Adult Patients with Schizophrenia and Bipolar I Mania — The efficacy of intramuscular olanzapine for injection in controlling agitation in these disorders was demonstrated in a dose range of 2.5 mg to 10 mg. The recommended dose in these patients is 10 mg. A lower dose of 5 or 7.5 mg may be considered when clinical factors warrant [see Clinical Studies (14.3)]. If agitation warranting additional intramuscular doses persists following the initial dose, subsequent doses up to 10 mg may be given. However, the efficacy of repeated doses of intramuscular olanzapine for injection in agitated patients has not been systematically evaluated in controlled clinical trials. Also, the safety of total daily doses greater than 30 mg, or 10 mg injections given more frequently than 2 hours after the initial dose, and 4 hours after the second dose have not been evaluated in clinical trials. Maximal dosing of intramuscular olanzapine (e.g., 3 doses of 10 mg administered 2-4 hours apart) may be associated with a substantial occurrence of significant orthostatic hypotension [see Warnings and Precautions (5.7)]. Thus, it is recommended that patients requiring subsequent intramuscular injections be assessed for orthostatic hypotension prior to the administration of any subsequent doses of intramuscular olanzapine for injection. The administration of an additional dose to a patient with a clinically significant postural change in systolic blood pressure is not recommended.

If ongoing olanzapine therapy is clinically indicated, oral olanzapine may be initiated in a range of 5-20 mg/day as soon as clinically appropriate [see Dosage and Administration (2.1, 2.2)].

Intramuscular Dosing in Special Populations — A dose of 5 mg/injection should be considered for geriatric patients or when other clinical factors warrant. A lower dose of 2.5 mg/injection should be considered for patients who otherwise might be debilitated, be predisposed to hypotensive reactions, or be more pharmacodynamically sensitive to olanzapine [see Warnings and Precautions (5.14), Drug Interactions (7), and Clinical Pharmacology (12.3)].

Administration of ZYPREXA IntraMuscular — ZYPREXA IntraMuscular is intended for intramuscular use only. Do not administer intravenously or subcutaneously. Inject slowly, deep into the muscle mass.

Parenteral drug products should be inspected visually for particulate matter and discoloration prior to administration, whenever solution and container permit.

Directions for Preparation of ZYPREXA IntraMuscular with Sterile Water for Injection — Dissolve the contents of the vial using 2.1 mL of Sterile Water for Injection to provide a solution containing approximately 5 mg/mL of olanzapine. The resulting solution should appear clear and yellow. ZYPREXA IntraMuscular reconstituted with Sterile Water for Injection should be used immediately (within 1 hour) after reconstitution. Discard any unused portion.

The following table provides injection volumes for delivering various doses of intramuscular olanzapine for injection reconstituted with Sterile Water for Injection.

Dose, mg Olanzapine | Volume of Injection, mL
10 | Withdraw total contents of vial
7.5 | 1.5
5 | 1
2.5 | 0.5

Physical Incompatibility Information — ZYPREXA IntraMuscular should be reconstituted only with Sterile Water for Injection. ZYPREXA IntraMuscular should not be combined in a syringe with diazepam injection because precipitation occurs when these products are mixed. Lorazepam injection should not be used to reconstitute ZYPREXA IntraMuscular as this combination results in a delayed reconstitution time. ZYPREXA IntraMuscular should not be combined in a syringe with haloperidol injection because the resulting low pH has been shown to degrade olanzapine over time.

2.5 ZYPREXA and Fluoxetine in Combination: Depressive Episodes Associated with Bipolar I Disorder

When using ZYPREXA and fluoxetine in combination, also refer to the Clinical Studies section of the package insert for Symbyax.

Adults

Oral olanzapine should be administered in combination with fluoxetine once daily in the evening, without regard to meals, generally beginning with 5 mg of oral olanzapine and 20 mg of fluoxetine. Dosage adjustments, if indicated, can be made according to efficacy and tolerability within dose ranges of oral olanzapine 5 to 12.5 mg and fluoxetine 20 to 50 mg. Antidepressant efficacy was demonstrated with ZYPREXA and fluoxetine in combination in adult patients with a dose range of olanzapine 6 to 12 mg and fluoxetine 25 to 50 mg. Safety of co-administration of doses above 18 mg olanzapine with 75 mg fluoxetine has not been evaluated in clinical studies.

Children and Adolescents (10-17 years of age)

Oral olanzapine should be administered in combination with fluoxetine once daily in the evening, without regard to meals, generally beginning with 2.5 mg of oral olanzapine and 20 mg of fluoxetine. Dosage adjustments, if indicated, can be made according to efficacy and tolerability. Safety of co-administration of doses above 12 mg olanzapine with 50 mg fluoxetine has not been evaluated in pediatric clinical studies.

Safety and efficacy of ZYPREXA and fluoxetine in combination was determined in clinical trials supporting approval of Symbyax (fixed dose combination of ZYPREXA and fluoxetine). Symbyax is dosed between 3 mg/25 mg (olanzapine/fluoxetine) per day and 12 mg/50 mg (olanzapine/fluoxetine) per day. The following table demonstrates the appropriate individual component doses of ZYPREXA and fluoxetine versus Symbyax. Dosage adjustments, if indicated, should be made with the individual components according to efficacy and tolerability.

Table 1: Approximate Dose Correspondence Between Symbyaxa and the Combination of ZYPREXA and Fluoxetine
For | Use in Combination
Symbyax | ZYPREXA | Fluoxetine
(mg/day) | (mg/day) | (mg/day)
3 mg olanzapine/25 mg fluoxetine | 2.5 | 20
6 mg olanzapine/25 mg fluoxetine | 5 | 20
12 mg olanzapine/25 mg fluoxetine | 10+2.5 | 20
6 mg olanzapine/50 mg fluoxetine | 5 | 40+10
12 mg olanzapine/50 mg fluoxetine | 10+2.5 | 40+10
a Symbyax (olanzapine/fluoxetine HCl) is a fixed-dose combination of ZYPREXA and fluoxetine.

While there is no body of evidence to answer the question of how long a patient treated with ZYPREXA and fluoxetine in combination should remain on it, it is generally accepted that bipolar I disorder, including the depressive episodes associated with bipolar I disorder, is a chronic illness requiring chronic treatment. The healthcare provider should periodically reexamine the need for continued pharmacotherapy.

ZYPREXA monotherapy is not indicated for the treatment of depressive episodes associated with bipolar I disorder.

2.6 ZYPREXA and Fluoxetine in Combination: Treatment Resistant Depression

When using ZYPREXA and fluoxetine in combination, also refer to the Clinical Studies section of the package insert for Symbyax.

Oral olanzapine should be administered in combination with fluoxetine once daily in the evening, without regard to meals, generally beginning with 5 mg of oral olanzapine and 20 mg of fluoxetine. Dosage adjustments, if indicated, can be made according to efficacy and tolerability within dose ranges of oral olanzapine 5 to 20 mg and fluoxetine 20 to 50 mg. Antidepressant efficacy was demonstrated with olanzapine and fluoxetine in combination in adult patients with a dose range of olanzapine 6 to 18 mg and fluoxetine 25 to 50 mg.

Safety and efficacy of olanzapine in combination with fluoxetine was determined in clinical trials supporting approval of Symbyax (fixed dose combination of olanzapine and fluoxetine). Symbyax is dosed between 3 mg/25 mg (olanzapine/fluoxetine) per day and 12 mg/50 mg (olanzapine/fluoxetine) per day. Table 1 above demonstrates the appropriate individual component doses of ZYPREXA and fluoxetine versus Symbyax. Dosage adjustments, if indicated, should be made with the individual components according to efficacy and tolerability.

While there is no body of evidence to answer the question of how long a patient treated with ZYPREXA and fluoxetine in combination should remain on it, it is generally accepted that treatment resistant depression (major depressive disorder in adult patients who do not respond to 2 separate trials of different antidepressants of adequate dose and duration in the current episode) is a chronic illness requiring chronic treatment. The healthcare provider should periodically reexamine the need for continued pharmacotherapy.

Safety of co-administration of doses above 18 mg olanzapine with 75 mg fluoxetine has not been evaluated in clinical studies.

ZYPREXA monotherapy is not indicated for treatment of treatment resistant depression (major depressive disorder in patients who do not respond to 2 antidepressants of adequate dose and duration in the current episode).

2.7 ZYPREXA and Fluoxetine in Combination: Dosing in Special Populations

The starting dose of oral olanzapine 2.5-5 mg with fluoxetine 20 mg should be used for patients with a predisposition to hypotensive reactions, patients with hepatic impairment, or patients who exhibit a combination of factors that may slow the metabolism of olanzapine or fluoxetine in combination (female gender, geriatric age, nonsmoking status), or those patients who may be pharmacodynamically sensitive to olanzapine. Dosing modification may be necessary in patients who exhibit a combination of factors that may slow metabolism. When indicated, dose escalation should be performed with caution in these patients. ZYPREXA and fluoxetine in combination have not been systematically studied in patients over 65 years of age or in patients under 10 years of age [see Warnings and Precautions (5.14), Drug Interactions (7), and Clinical Pharmacology (12.3)].

3 DOSAGE FORMS AND STRENGTHS

The ZYPREXA 2.5 mg, 5 mg, 7.5 mg, and 10 mg tablets are white, round, and imprinted in blue ink with LILLY and tablet number. The 15 mg tablets are elliptical, blue, and debossed with LILLY and tablet number. The 20 mg tablets are elliptical, pink, and debossed with LILLY and tablet number. Tablets are not scored. The tablets are available as follows:

 | TABLET STRENGTH
 | 2.5 mg | 5 mg | 7.5 mg | 10 mg | 15 mg | 20 mg
Tablet No. | 4112 | 4115 | 4116 | 4117 | 4415 | 4420
Identification | LILLY | LILLY | LILLY | LILLY | LILLY | LILLY
 | 4112 | 4115 | 4116 | 4117 | 4415 | 4420

ZYPREXA ZYDIS (olanzapine orally disintegrating tablets) are yellow, round, and debossed with the tablet strength. Tablets are not scored. The tablets are available as follows:

 | TABLET STRENGTH
ZYPREXA ZYDIS Tablets | 5 mg | 10 mg | 15 mg | 20 mg
Tablet No. | 4453 | 4454 | 4455 | 4456
Debossed | 5 | 10 | 15 | 20

ZYPREXA IntraMuscular is available as single-dose 10 mg vial (1s).

4 CONTRAINDICATIONS

- None with ZYPREXA monotherapy.
- When using ZYPREXA and fluoxetine in combination, also refer to the Contraindications section of the package insert for Symbyax.
- For specific information about the contraindications of lithium or valproate, refer to the Contraindications section of the package inserts for these other products.

5 WARNINGS AND PRECAUTIONS

When using ZYPREXA and fluoxetine in combination, also refer to the Warnings and Precautions section of the package insert for Symbyax.

5.1 Elderly Patients with Dementia-Related Psychosis

Increased Mortality — Elderly patients with dementia-related psychosis treated with antipsychotic drugs are at an increased risk of death. ZYPREXA is not approved for the treatment of patients with dementia-related psychosis [see Boxed Warning, Use in Specific Populations (8.5), and Patient Counseling Information (17)].

In placebo-controlled clinical trials of elderly patients with dementia-related psychosis, the incidence of death in olanzapine-treated patients was significantly greater than placebo-treated patients (3.5% vs 1.5%, respectively).

Cerebrovascular Adverse Events (CVAE), Including Stroke — Cerebrovascular adverse events (e.g., stroke, transient ischemic attack), including fatalities, were reported in patients in trials of olanzapine in elderly patients with dementia-related psychosis. In placebo-controlled trials, there was a significantly higher incidence of cerebrovascular adverse events in patients treated with olanzapine compared to patients treated with placebo. Olanzapine is not approved for the treatment of patients with dementia-related psychosis [see Boxed Warning and Patient Counseling Information (17)].

5.2 Suicide

The possibility of a suicide attempt is inherent in schizophrenia and in bipolar I disorder, and close supervision of high-risk patients should accompany drug therapy. Prescriptions for olanzapine should be written for the smallest quantity of tablets consistent with good patient management, in order to reduce the risk of overdose.

5.3 Neuroleptic Malignant Syndrome (NMS)

A potentially fatal symptom complex sometimes referred to as Neuroleptic Malignant Syndrome (NMS) has been reported in association with administration of antipsychotic drugs, including olanzapine. Clinical manifestations of NMS are hyperpyrexia, muscle rigidity, altered mental status and evidence of autonomic instability (irregular pulse or blood pressure, tachycardia, diaphoresis and cardiac dysrhythmia). Additional signs may include elevated creatinine phosphokinase, myoglobinuria (rhabdomyolysis), and acute renal failure.

The diagnostic evaluation of patients with this syndrome is complicated. In arriving at a diagnosis, it is important to exclude cases where the clinical presentation includes both serious medical illness (e.g., pneumonia, systemic infection, etc.) and untreated or inadequately treated extrapyramidal signs and symptoms (EPS). Other important considerations in the differential diagnosis include central anticholinergic toxicity, heat stroke, drug fever, and primary central nervous system pathology.

The management of NMS should include: 1) immediate discontinuation of antipsychotic drugs and other drugs not essential to concurrent therapy; 2) intensive symptomatic treatment and medical monitoring; and 3) treatment of any concomitant serious medical problems for which specific treatments are available. There is no general agreement about specific pharmacological treatment regimens for NMS.

If a patient requires antipsychotic drug treatment after recovery from NMS, the potential reintroduction of drug therapy should be carefully considered. The patient should be carefully monitored, since recurrences of NMS have been reported [see Patient Counseling Information (17)].

5.4 Drug Reaction with Eosinophilia and Systemic Symptoms (DRESS)

Drug reaction with eosinophilia and systemic symptoms (DRESS) has been reported with olanzapine exposure. DRESS may present with a cutaneous reaction (such as rash or exfoliative dermatitis), eosinophilia, fever, and/or lymphadenopathy with systemic complications such as hepatitis, nephritis, pneumonitis, myocarditis, and/or pericarditis. DRESS is sometimes fatal. Discontinue olanzapine if DRESS is suspected [see Patient Counseling Information (17)].

5.5 Metabolic Changes

Atypical antipsychotic drugs have been associated with metabolic changes including hyperglycemia, dyslipidemia, and weight gain. Metabolic changes may be associated with increased cardiovascular/cerebrovascular risk. Olanzapine's specific metabolic profile is presented below.

Hyperglycemia and Diabetes Mellitus

Healthcare providers should consider the risks and benefits when prescribing olanzapine to patients with an established diagnosis of diabetes mellitus, or having borderline increased blood glucose level (fasting 100-126 mg/dL, nonfasting 140-200 mg/dL). Patients taking olanzapine should be monitored regularly for worsening of glucose control. Patients starting treatment with olanzapine should undergo fasting blood glucose testing at the beginning of treatment and periodically during treatment. Any patient treated with atypical antipsychotics should be monitored for symptoms of hyperglycemia including polydipsia, polyuria, polyphagia, and weakness. Patients who develop symptoms of hyperglycemia during treatment with atypical antipsychotics should undergo fasting blood glucose testing. In some cases, hyperglycemia has resolved when the atypical antipsychotic was discontinued; however, some patients required continuation of anti-diabetic treatment despite discontinuation of the suspect drug [see Patient Counseling Information (17)].

Hyperglycemia, in some cases extreme and associated with ketoacidosis or hyperosmolar coma or death, has been reported in patients treated with atypical antipsychotics including olanzapine. Assessment of the relationship between atypical antipsychotic use and glucose abnormalities is complicated by the possibility of an increased background risk of diabetes mellitus in patients with schizophrenia and the increasing incidence of diabetes mellitus in the general population. Epidemiological studies suggest an increased risk of treatment-emergent hyperglycemia-related adverse reactions in patients treated with the atypical antipsychotics. While relative risk estimates are inconsistent, the association between atypical antipsychotics and increases in glucose levels appears to fall on a continuum and olanzapine appears to have a greater association than some other atypical antipsychotics.

Mean increases in blood glucose have been observed in patients treated (median exposure of 9.2 months) with olanzapine in phase 1 of the Clinical Antipsychotic Trials of Intervention Effectiveness (CATIE). The mean increase of serum glucose (fasting and nonfasting samples) from baseline to the average of the 2 highest serum concentrations was 15.0 mg/dL.

In a study of healthy volunteers, subjects who received olanzapine (N=22) for 3 weeks had a mean increase compared to baseline in fasting blood glucose of 2.3 mg/dL. Placebo-treated subjects (N=19) had a mean increase in fasting blood glucose compared to baseline of 0.34 mg/dL.

Olanzapine Monotherapy in Adults — In an analysis of 5 placebo-controlled adult olanzapine monotherapy studies with a median treatment duration of approximately 3 weeks, olanzapine was associated with a greater mean change in fasting glucose levels compared to placebo (2.76 mg/dL versus 0.17 mg/dL). The difference in mean changes between olanzapine and placebo was greater in patients with evidence of glucose dysregulation at baseline (patients diagnosed with diabetes mellitus or related adverse reactions, patients treated with anti-diabetic agents, patients with a baseline random glucose level ≥200 mg/dL, and/or a baseline fasting glucose level ≥126 mg/dL). Olanzapine-treated patients had a greater mean HbA1c increase from baseline of 0.04% (median exposure 21 days), compared to a mean HbA1c decrease of 0.06% in placebo-treated subjects (median exposure 17 days).

In an analysis of 8 placebo-controlled studies (median treatment exposure 4-5 weeks), 6.1% of olanzapine-treated subjects (N=855) had treatment-emergent glycosuria compared to 2.8% of placebo-treated subjects (N=599). Table 2 shows short-term and long-term changes in fasting glucose levels from adult olanzapine monotherapy studies.

Table 2: Changes in Fasting Glucose Levels from Adult Olanzapine Monotherapy Studies
 |  |  | Up to 12 weeks exposure |  | At least 48 weeks exposure
Laboratory Analyte | Category Change (at least once) from Baseline | Treatment Arm | N | Patients | N | Patients
Fasting Glucose | Normal to High (<100 mg/dL to ≥126 mg/dL) | Olanzapine | 543 | 2.2% | 345 | 12.8%
Fasting Glucose | Normal to High (<100 mg/dL to ≥126 mg/dL) | Placebo | 293 | 3.4% | NAa | NAa
Fasting Glucose | Borderline to High (≥100 mg/dL and <126 mg/dL to ≥126 mg/dL) | Olanzapine | 178 | 17.4% | 127 | 26.0%
Fasting Glucose | Borderline to High (≥100 mg/dL and <126 mg/dL to ≥126 mg/dL) | Placebo | 96 | 11.5% | NAa | NAa
a Not Applicable.

The mean change in fasting glucose for patients exposed at least 48 weeks was 4.2 mg/dL (N=487). In analyses of patients who completed 9-12 months of olanzapine therapy, mean change in fasting and nonfasting glucose levels continued to increase over time.

Olanzapine Monotherapy in Adolescents — The safety and efficacy of olanzapine have not been established in patients under the age of 13 years. In an analysis of 3 placebo-controlled olanzapine monotherapy studies of adolescent patients, including those with schizophrenia (6 weeks) or bipolar I disorder (manic or mixed episodes) (3 weeks), olanzapine was associated with a greater mean change from baseline in fasting glucose levels compared to placebo (2.68 mg/dL versus -2.59 mg/dL). The mean change in fasting glucose for adolescents exposed at least 24 weeks was 3.1 mg/dL (N=121). Table 3 shows short-term and long-term changes in fasting blood glucose from adolescent olanzapine monotherapy studies.

Table 3: Changes in Fasting Glucose Levels from Adolescent Olanzapine Monotherapy Studies
 |  |  | Up to 12 weeks exposure |  | At least 24 weeks exposure
Laboratory Analyte | Category Change (at least once) from Baseline | Treatment Arm | N | Patients | N | Patients
Fasting Glucose | Normal to High (<100 mg/dL to ≥126 mg/dL) | Olanzapine | 124 | 0% | 108 | 0.9%
Fasting Glucose | Normal to High (<100 mg/dL to ≥126 mg/dL) | Placebo | 53 | 1.9% | NAa | NAa
Fasting Glucose | Borderline to High (≥100 mg/dL and <126 mg/dL to ≥126 mg/dL) | Olanzapine | 14 | 14.3% | 13 | 23.1%
Fasting Glucose | Borderline to High (≥100 mg/dL and <126 mg/dL to ≥126 mg/dL) | Placebo | 13 | 0% | NAa | NAa
a Not Applicable.

Dyslipidemia

Undesirable alterations in lipids have been observed with olanzapine use. Clinical monitoring, including baseline and periodic follow-up lipid evaluations in patients using olanzapine, is recommended [see Patient Counseling Information (17)].

Clinically significant, and sometimes very high (>500 mg/dL), elevations in triglyceride levels have been observed with olanzapine use. Modest mean increases in total cholesterol have also been seen with olanzapine use.

Olanzapine Monotherapy in Adults — In an analysis of 5 placebo-controlled olanzapine monotherapy studies with treatment duration up to 12 weeks, olanzapine-treated patients had increases from baseline in mean fasting total cholesterol, LDL cholesterol, and triglycerides of 5.3 mg/dL, 3.0 mg/dL, and 20.8 mg/dL respectively compared to decreases from baseline in mean fasting total cholesterol, LDL cholesterol, and triglycerides of 6.1 mg/dL, 4.3 mg/dL, and 10.7 mg/dL for placebo-treated patients. For fasting HDL cholesterol, no clinically meaningful differences were observed between olanzapine-treated patients and placebo-treated patients. Mean increases in fasting lipid values (total cholesterol, LDL cholesterol, and triglycerides) were greater in patients without evidence of lipid dysregulation at baseline, where lipid dysregulation was defined as patients diagnosed with dyslipidemia or related adverse reactions, patients treated with lipid lowering agents, or patients with high baseline lipid levels.

In long-term studies (at least 48 weeks), patients had increases from baseline in mean fasting total cholesterol, LDL cholesterol, and triglycerides of 5.6 mg/dL, 2.5 mg/dL, and 18.7 mg/dL, respectively, and a mean decrease in fasting HDL cholesterol of 0.16 mg/dL. In an analysis of patients who completed 12 months of therapy, the mean nonfasting total cholesterol did not increase further after approximately 4-6 months.

The proportion of patients who had changes (at least once) in total cholesterol, LDL cholesterol or triglycerides from normal or borderline to high, or changes in HDL cholesterol from normal or borderline to low, was greater in long-term studies (at least 48 weeks) as compared with short-term studies. Table 4 shows categorical changes in fasting lipids values.

Table 4: Changes in Fasting Lipids Values from Adult Olanzapine Monotherapy Studies
 |  |  | Up to 12 weeks exposure |  | At least 48 weeks exposure
Laboratory Analyte | Category Change (at least once) from Baseline | Treatment Arm | N | Patients | N | Patients
Fasting Triglycerides | Increase by ≥50 mg/dL | Olanzapine | 745 | 39.6% | 487 | 61.4%
Fasting Triglycerides | Increase by ≥50 mg/dL | Placebo | 402 | 26.1% | NAa | NAa
Fasting Triglycerides | Normal to High (<150 mg/dL to ≥200 mg/dL) | Olanzapine | 457 | 9.2% | 293 | 32.4%
Fasting Triglycerides | Normal to High (<150 mg/dL to ≥200 mg/dL) | Placebo | 251 | 4.4% | NAa | NAa
Fasting Triglycerides | Borderline to High (≥150 mg/dL and <200 mg/dL to ≥200 mg/dL) | Olanzapine | 135 | 39.3% | 75 | 70.7%
Fasting Triglycerides | Borderline to High (≥150 mg/dL and <200 mg/dL to ≥200 mg/dL) | Placebo | 65 | 20.0% | NAa | NAa
Fasting Total Cholesterol | Increase by ≥40 mg/dL | Olanzapine | 745 | 21.6% | 489 | 32.9%
Fasting Total Cholesterol | Increase by ≥40 mg/dL | Placebo | 402 | 9.5% | NAa | NAa
Fasting Total Cholesterol | Normal to High (<200 mg/dL to ≥240 mg/dL) | Olanzapine | 392 | 2.8% | 283 | 14.8%
Fasting Total Cholesterol | Normal to High (<200 mg/dL to ≥240 mg/dL) | Placebo | 207 | 2.4% | NAa | NAa
Fasting Total Cholesterol | Borderline to High (≥200 mg/dL and <240 mg/dL to ≥240 mg/dL) | Olanzapine | 222 | 23.0% | 125 | 55.2%
Fasting Total Cholesterol | Borderline to High (≥200 mg/dL and <240 mg/dL to ≥240 mg/dL) | Placebo | 112 | 12.5% | NAa | NAa
Fasting LDL Cholesterol | Increase by ≥30 mg/dL | Olanzapine | 536 | 23.7% | 483 | 39.8%
Fasting LDL Cholesterol | Increase by ≥30 mg/dL | Placebo | 304 | 14.1% | NAa | NAa
Fasting LDL Cholesterol | Normal to High (<100 mg/dL to ≥160 mg/dL) | Olanzapine | 154 | 0% | 123 | 7.3%
Fasting LDL Cholesterol | Normal to High (<100 mg/dL to ≥160 mg/dL) | Placebo | 82 | 1.2% | NAa | NAa
Fasting LDL Cholesterol | Borderline to High (≥100 mg/dL and <160 mg/dL to ≥160 mg/dL) | Olanzapine | 302 | 10.6% | 284 | 31.0%
Fasting LDL Cholesterol | Borderline to High (≥100 mg/dL and <160 mg/dL to ≥160 mg/dL) | Placebo | 173 | 8.1% | NAa | NAa
a Not Applicable.

In phase 1 of the Clinical Antipsychotic Trials of Intervention Effectiveness (CATIE), over a median exposure of 9.2 months, the mean increase in triglycerides in patients taking olanzapine was 40.5 mg/dL. In phase 1 of CATIE, the mean increase in total cholesterol was 9.4 mg/dL.

Olanzapine Monotherapy in Adolescents — The safety and efficacy of olanzapine have not been established in patients under the age of 13 years. In an analysis of 3 placebo-controlled olanzapine monotherapy studies of adolescents, including those with schizophrenia (6 weeks) or bipolar I disorder (manic or mixed episodes) (3 weeks), olanzapine-treated adolescents had increases from baseline in mean fasting total cholesterol, LDL cholesterol, and triglycerides of 12.9 mg/dL, 6.5 mg/dL, and 28.4 mg/dL, respectively, compared to increases from baseline in mean fasting total cholesterol and LDL cholesterol of 1.3 mg/dL and 1.0 mg/dL, and a decrease in triglycerides of 1.1 mg/dL for placebo-treated adolescents. For fasting HDL cholesterol, no clinically meaningful differences were observed between olanzapine-treated adolescents and placebo-treated adolescents.

In long-term studies (at least 24 weeks), adolescents had increases from baseline in mean fasting total cholesterol, LDL cholesterol, and triglycerides of 5.5 mg/dL, 5.4 mg/dL, and 20.5 mg/dL, respectively, and a mean decrease in fasting HDL cholesterol of 4.5 mg/dL. Table 5 shows categorical changes in fasting lipids values in adolescents.

Table 5: Changes in Fasting Lipids Values from Adolescent Olanzapine Monotherapy Studies
 |  |  | Up to 6 weeks exposure |  | At least 24 weeks exposure
Laboratory Analyte | Category Change (at least once) from Baseline | Treatment Arm | N | Patients | N | Patients
Fasting Triglycerides | Increase by ≥50 mg/dL | Olanzapine | 138 | 37.0% | 122 | 45.9%
Fasting Triglycerides | Increase by ≥50 mg/dL | Placebo | 66 | 15.2% | NAa | NAa
Fasting Triglycerides | Normal to High (<90 mg/dL to >130 mg/dL) | Olanzapine | 67 | 26.9% | 66 | 36.4%
Fasting Triglycerides | Normal to High (<90 mg/dL to >130 mg/dL) | Placebo | 28 | 10.7% | NAa | NAa
Fasting Triglycerides | Borderline to High (≥90 mg/dL and ≤130 mg/dL to >130 mg/dL) | Olanzapine | 37 | 59.5% | 31 | 64.5%
Fasting Triglycerides | Borderline to High (≥90 mg/dL and ≤130 mg/dL to >130 mg/dL) | Placebo | 17 | 35.3% | NAa | NAa
Fasting Total Cholesterol | Increase by ≥40 mg/dL | Olanzapine | 138 | 14.5% | 122 | 14.8%
Fasting Total Cholesterol | Increase by ≥40 mg/dL | Placebo | 66 | 4.5% | NAa | NAa
Fasting Total Cholesterol | Normal to High (<170 mg/dL to ≥200 mg/dL) | Olanzapine | 87 | 6.9% | 78 | 7.7%
Fasting Total Cholesterol | Normal to High (<170 mg/dL to ≥200 mg/dL) | Placebo | 43 | 2.3% | NAa | NAa
Fasting Total Cholesterol | Borderline to High (≥170 mg/dL and <200 mg/dL to ≥200 mg/dL) | Olanzapine | 36 | 38.9% | 33 | 57.6%
Fasting Total Cholesterol | Borderline to High (≥170 mg/dL and <200 mg/dL to ≥200 mg/dL) | Placebo | 13 | 7.7% | NAa | NAa
Fasting LDL Cholesterol | Increase by ≥30 mg/dL | Olanzapine | 137 | 17.5% | 121 | 22.3%
Fasting LDL Cholesterol | Increase by ≥30 mg/dL | Placebo | 63 | 11.1% | NAa | NAa
Fasting LDL Cholesterol | Normal to High (<110 mg/dL to ≥130 mg/dL) | Olanzapine | 98 | 5.1% | 92 | 10.9%
Fasting LDL Cholesterol | Normal to High (<110 mg/dL to ≥130 mg/dL) | Placebo | 44 | 4.5% | NAa | NAa
Fasting LDL Cholesterol | Borderline to High (≥110 mg/dL and <130 mg/dL to ≥130 mg/dL) | Olanzapine | 29 | 48.3% | 21 | 47.6%
Fasting LDL Cholesterol | Borderline to High (≥110 mg/dL and <130 mg/dL to ≥130 mg/dL) | Placebo | 9 | 0% | NAa | NAa
a Not Applicable.

Weight Gain

Potential consequences of weight gain should be considered prior to starting olanzapine. Patients receiving olanzapine should receive regular monitoring of weight [see Patient Counseling Information (17)].

Olanzapine Monotherapy in Adults — In an analysis of 13 placebo-controlled olanzapine monotherapy studies, olanzapine-treated patients gained an average of 2.6 kg (5.7 lb) compared to an average 0.3 kg (0.6 lb) weight loss in placebo-treated patients with a median exposure of 6 weeks; 22.2% of olanzapine-treated patients gained at least 7% of their baseline weight, compared to 3% of placebo-treated patients, with a median exposure to event of 8 weeks; 4.2% of olanzapine-treated patients gained at least 15% of their baseline weight, compared to 0.3% of placebo-treated patients, with a median exposure to event of 12 weeks. Clinically significant weight gain was observed across all baseline Body Mass Index (BMI) categories. Discontinuation due to weight gain occurred in 0.2% of olanzapine-treated patients and in 0% of placebo-treated patients.

In long-term studies (at least 48 weeks), the mean weight gain was 5.6 kg (12.3 lb) (median exposure of 573 days, N=2021). The percentages of patients who gained at least 7%, 15%, or 25% of their baseline body weight with long-term exposure were 64%, 32%, and 12%, respectively. Discontinuation due to weight gain occurred in 0.4% of olanzapine-treated patients following at least 48 weeks of exposure.

Table 6 includes data on adult weight gain with olanzapine pooled from 86 clinical trials. The data in each column represent data for those patients who completed treatment periods of the durations specified.

Table 6: Weight Gain with Olanzapine Use in Adults
Amount Gained kg (lb) | 6 Weeks (N=7465) (%) | 6 Months (N=4162) (%) | 12 Months (N=1345) (%) | 24 Months (N=474) (%) | 36 Months (N=147) (%)
≤0 | 26.2 | 24.3 | 20.8 | 23.2 | 17.0
0 to ≤5 (0-11 lb) | 57.0 | 36.0 | 26.0 | 23.4 | 25.2
>5 to ≤10 (11-22 lb) | 14.9 | 24.6 | 24.2 | 24.1 | 18.4
>10 to ≤15 (22-33 lb) | 1.8 | 10.9 | 14.9 | 11.4 | 17.0
>15 to ≤20 (33-44 lb) | 0.1 | 3.1 | 8.6 | 9.3 | 11.6
>20 to ≤25 (44-55 lb) | 0 | 0.9 | 3.3 | 5.1 | 4.1
>25 to ≤30 (55-66 lb) | 0 | 0.2 | 1.4 | 2.3 | 4.8
>30 (>66 lb) | 0 | 0.1 | 0.8 | 1.2 | 2

Dose group differences with respect to weight gain have been observed. In a single 8-week randomized, double-blind, fixed-dose study comparing 10 (N=199), 20 (N=200) and 40 (N=200) mg/day of oral olanzapine in adult patients with schizophrenia or schizoaffective disorder, mean baseline to endpoint increase in weight (10 mg/day: 1.9 kg; 20 mg/day: 2.3 kg; 40 mg/day: 3 kg) was observed with significant differences between 10 vs 40 mg/day.

Olanzapine Monotherapy in Adolescents — The safety and efficacy of olanzapine have not been established in patients under the age of 13 years. Mean increase in weight in adolescents was greater than in adults. In 4 placebo-controlled trials, discontinuation due to weight gain occurred in 1% of olanzapine-treated patients, compared to 0% of placebo-treated patients.

Table 7: Weight Gain with Olanzapine Use in Adolescents from 4 Placebo-Controlled Trials
 | Olanzapine-treated patients | Placebo-treated patients
Mean change in body weight from baseline (median exposure = 3 weeks) | 4.6 kg (10.1 lb) | 0.3 kg (0.7 lb)
Percentage of patients who gained at least 7% of baseline body weight | 40.6% | 9.8%
Percentage of patients who gained at least 7% of baseline body weight | (median exposure to 7% = 4 weeks) | (median exposure to 7% = 8 weeks)
Percentage of patients who gained at least 15% of baseline body weight | 7.1% | 2.7%
Percentage of patients who gained at least 15% of baseline body weight | (median exposure to 15% = 19 weeks) | (median exposure to 15% = 8 weeks)

In long-term studies (at least 24 weeks), the mean weight gain was 11.2 kg (24.6 lb); (median exposure of 201 days, N=179). The percentages of adolescents who gained at least 7%, 15%, or 25% of their baseline body weight with long-term exposure were 89%, 55%, and 29%, respectively. Among adolescent patients, mean weight gain by baseline BMI category was 11.5 kg (25.3 lb), 12.1 kg (26.6 lb), and 12.7 kg (27.9 lb), respectively, for normal (N=106), overweight (N=26) and obese (N=17). Discontinuation due to weight gain occurred in 2.2% of olanzapine-treated patients following at least 24 weeks of exposure.

Table 8 shows data on adolescent weight gain with olanzapine pooled from 6 clinical trials. The data in each column represent data for those patients who completed treatment periods of the durations specified. Little clinical trial data is available on weight gain in adolescents with olanzapine beyond 6 months of treatment.

Table 8: Weight Gain with Olanzapine Use in Adolescents
Amount Gained kg (lb) | 6 Weeks (N=243) (%) | 6 Months (N=191) (%)
≤0 | 2.9 | 2.1
0 to ≤5 (0-11 lb) | 47.3 | 24.6
>5 to ≤10 (11-22 lb) | 42.4 | 26.7
>10 to ≤15 (22-33 lb) | 5.8 | 22.0
>15 to ≤20 (33-44 lb) | 0.8 | 12.6
>20 to ≤25 (44-55 lb) | 0.8 | 9.4
>25 to ≤30 (55-66 lb) | 0 | 2.1
>30 to ≤35 (66-77 lb) | 0 | 0
>35 to ≤40 (77-88 lb) | 0 | 0
>40 (>88 lb) | 0 | 0.5

5.6 Tardive Dyskinesia

A syndrome of potentially irreversible, involuntary, dyskinetic movements may develop in patients treated with antipsychotic drugs. Although the prevalence of the syndrome appears to be highest among the elderly, especially elderly women, it is impossible to rely upon prevalence estimates to predict, at the inception of antipsychotic treatment, which patients are likely to develop the syndrome. Whether antipsychotic drug products differ in their potential to cause tardive dyskinesia is unknown.

The risk of developing tardive dyskinesia and the likelihood that it will become irreversible are believed to increase as the duration of treatment and the total cumulative dose of antipsychotic drugs administered to the patient increase. However, the syndrome can develop, although much less commonly, after relatively brief treatment periods at low doses or may even arise after discontinuation of treatment.

Tardive dyskinesia may remit, partially or completely, if antipsychotic treatment is withdrawn. Antipsychotic treatment, itself, however, may suppress (or partially suppress) the signs and symptoms of the syndrome and thereby may possibly mask the underlying process. The effect that symptomatic suppression has upon the long-term course of the syndrome is unknown.

Given these considerations, olanzapine should be prescribed in a manner that is most likely to minimize the occurrence of tardive dyskinesia. Chronic antipsychotic treatment should generally be reserved for patients (1) who suffer from a chronic illness that is known to respond to antipsychotic drugs, and (2) for whom alternative, equally effective, but potentially less harmful treatments are not available or appropriate. In patients who do require chronic treatment, the smallest dose and the shortest duration of treatment producing a satisfactory clinical response should be sought. The need for continued treatment should be reassessed periodically.

If signs and symptoms of tardive dyskinesia appear in a patient on olanzapine, drug discontinuation should be considered. However, some patients may require treatment with olanzapine despite the presence of the syndrome.

For specific information about the warnings of lithium or valproate, refer to the Warnings section of the package inserts for these other products.

5.7 Orthostatic Hypotension

Olanzapine may induce orthostatic hypotension associated with dizziness, tachycardia, bradycardia and, in some patients, syncope, especially during the initial dose-titration period, probably reflecting its α1-adrenergic antagonistic properties [see Patient Counseling Information (17)].

From an analysis of the vital sign data in an integrated database of 41 completed clinical studies in adult patients treated with oral olanzapine, orthostatic hypotension was recorded in ≥20% (1277/6030) of patients.

For oral olanzapine therapy, the risk of orthostatic hypotension and syncope may be minimized by initiating therapy with 5 mg QD [see Dosage and Administration (2)]. A more gradual titration to the target dose should be considered if hypotension occurs.

Hypotension, bradycardia with or without hypotension, tachycardia, and syncope were also reported during the clinical trials with intramuscular olanzapine for injection. In an open-label clinical pharmacology study in nonagitated patients with schizophrenia in which the safety and tolerability of intramuscular olanzapine were evaluated under a maximal dosing regimen (three 10 mg doses administered 4 hours apart), approximately one-third of these patients experienced a significant orthostatic decrease in systolic blood pressure (i.e., decrease ≥30 mmHg) [see Dosage and Administration (2.4)]. Syncope was reported in 0.6% (15/2500) of olanzapine-treated patients in phase 2-3 oral olanzapine studies and in 0.3% (2/722) of olanzapine-treated patients with agitation in the intramuscular olanzapine for injection studies. Three normal volunteers in phase 1 studies with intramuscular olanzapine experienced hypotension, bradycardia, and sinus pauses of up to 6 seconds that spontaneously resolved (in 2 cases the reactions occurred on intramuscular olanzapine, and in 1 case, on oral olanzapine). The risk for this sequence of hypotension, bradycardia, and sinus pause may be greater in nonpsychiatric patients compared to psychiatric patients who are possibly more adapted to certain effects of psychotropic drugs. For intramuscular olanzapine for injection therapy, patients should remain recumbent if drowsy or dizzy after injection until examination has indicated that they are not experiencing postural hypotension, bradycardia, and/or hypoventilation.

Olanzapine should be used with particular caution in patients with known cardiovascular disease (history of myocardial infarction or ischemia, heart failure, or conduction abnormalities), cerebrovascular disease, and conditions which would predispose patients to hypotension (dehydration, hypovolemia, and treatment with antihypertensive medications) where the occurrence of syncope, or hypotension and/or bradycardia might put the patient at increased medical risk.

Caution is necessary in patients who receive treatment with other drugs having effects that can induce hypotension, bradycardia, respiratory or central nervous system depression [see Drug Interactions (7)]. Concomitant administration of intramuscular olanzapine and parenteral benzodiazepine is not recommended due to the potential for excessive sedation and cardiorespiratory depression.

5.8 Falls

ZYPREXA may cause somnolence, postural hypotension, motor and sensory instability, which may lead to falls and, consequently, fractures or other injuries. For patients with diseases, conditions, or medications that could exacerbate these effects, complete fall risk assessments when initiating antipsychotic treatment and recurrently for patients on long-term antipsychotic therapy.

5.9 Leukopenia, Neutropenia, and Agranulocytosis

Class Effect — In clinical trial and/or postmarketing experience, events of leukopenia/neutropenia have been reported temporally related to antipsychotic agents, including ZYPREXA. Agranulocytosis has also been reported.

Possible risk factors for leukopenia/neutropenia include pre-existing low white blood cell count (WBC) and history of drug induced leukopenia/neutropenia. Patients with a history of a clinically significant low WBC or drug induced leukopenia/neutropenia should have their complete blood count (CBC) monitored frequently during the first few months of therapy and discontinuation of ZYPREXA should be considered at the first sign of a clinically significant decline in WBC in the absence of other causative factors.

Patients with clinically significant neutropenia should be carefully monitored for fever or other symptoms or signs of infection and treated promptly if such symptoms or signs occur. Patients with severe neutropenia (absolute neutrophil count <1000/mm^3) should discontinue ZYPREXA and have their WBC followed until recovery.

5.10 Dysphagia

Esophageal dysmotility and aspiration have been associated with antipsychotic drug use. Aspiration pneumonia is a common cause of morbidity and mortality in patients with advanced Alzheimer's disease. Olanzapine is not approved for the treatment of patients with Alzheimer's disease.

5.11 Seizures

During premarketing testing, seizures occurred in 0.9% (22/2500) of olanzapine-treated patients. There were confounding factors that may have contributed to the occurrence of seizures in many of these cases. Olanzapine should be used cautiously in patients with a history of seizures or with conditions that potentially lower the seizure threshold, e.g., Alzheimer's dementia. Olanzapine is not approved for the treatment of patients with Alzheimer's disease. Conditions that lower the seizure threshold may be more prevalent in a population of 65 years or older.

5.12 Potential for Cognitive and Motor Impairment

Somnolence was a commonly reported adverse reaction associated with olanzapine treatment, occurring at an incidence of 26% in olanzapine patients compared to 15% in placebo patients. This adverse reaction was also dose related. Somnolence led to discontinuation in 0.4% (9/2500) of patients in the premarketing database.

Since olanzapine has the potential to impair judgment, thinking, or motor skills, patients should be cautioned about operating hazardous machinery, including automobiles, until they are reasonably certain that olanzapine therapy does not affect them adversely [see Patient Counseling Information (17)].

5.13 Body Temperature Regulation

Disruption of the body's ability to reduce core body temperature has been attributed to antipsychotic agents. Appropriate care is advised when prescribing olanzapine for patients who will be experiencing conditions which may contribute to an elevation in core body temperature, e.g., exercising strenuously, exposure to extreme heat, receiving concomitant medication with anticholinergic activity, or being subject to dehydration [see Patient Counseling Information (17)].

5.14 Anticholinergic (antimuscarinic) Effects

Olanzapine exhibits in vitro muscarinic receptor affinity [see Clinical Pharmacology 12.2]. In premarketing clinical trials, Zyprexa was associated with constipation, dry mouth, and tachycardia, all adverse reactions possibly related to cholinergic antagonism. Such adverse reactions were not often the basis for discontinuations, but Zyprexa should be used with caution in patients with a current diagnosis or prior history of urinary retention, clinically significant prostatic hypertrophy, constipation, or a history of paralytic ileus or related conditions. In post marketing experience, the risk for severe adverse reactions (including fatalities) was increased with concomitant use of anticholinergic medications [see Drug Interactions (7.1)].

5.15 Hyperprolactinemia

As with other drugs that antagonize dopamine D2 receptors, olanzapine elevates prolactin levels, and the elevation persists during chronic administration. Hyperprolactinemia may suppress hypothalamic GnRH, resulting in reduced pituitary gonadotropin secretion. This, in turn, may inhibit reproductive function by impairing gonadal steroidogenesis in both female and male patients. Galactorrhea, amenorrhea, gynecomastia, and impotence have been reported in patients receiving prolactin-elevating compounds. Long-standing hyperprolactinemia when associated with hypogonadism may lead to decreased bone density in both female and male subjects.

Tissue culture experiments indicate that approximately one-third of human breast cancers are prolactin dependent in vitro, a factor of potential importance if the prescription of these drugs is contemplated in a patient with previously detected breast cancer. As is common with compounds which increase prolactin release, an increase in mammary gland neoplasia was observed in the olanzapine carcinogenicity studies conducted in mice and rats [see Nonclinical Toxicology (13.1)]. Published epidemiologic studies have shown inconsistent results when exploring the potential association between hyperprolactinemia and breast cancer.

In placebo-controlled olanzapine clinical studies (up to 12 weeks), changes from normal to high in prolactin concentrations were observed in 30% of adults treated with olanzapine as compared to 10.5% of adults treated with placebo. In a pooled analysis from clinical studies including 8136 adults treated with olanzapine, potentially associated clinical manifestations included menstrual-related events^1 (2% [49/3240] of females), sexual function-related events^2 (2% [150/8136] of females and males), and breast-related events^3 (0.7% [23/3240] of females, 0.2% [9/4896] of males).

In placebo-controlled olanzapine monotherapy studies in adolescent patients (up to 6 weeks) with schizophrenia or bipolar I disorder (manic or mixed episodes), changes from normal to high in prolactin concentrations were observed in 47% of olanzapine-treated patients compared to 7% of placebo-treated patients. In a pooled analysis from clinical trials including 454 adolescents treated with olanzapine, potentially associated clinical manifestations included menstrual-related events^1 (1% [2/168] of females), sexual function-related events^2 (0.7% [3/454] of females and males), and breast-related events^3 (2% [3/168] of females, 2% [7/286] of males) [see Use in Specific Populations (8.4)].

^1 Based on a search of the following terms: amenorrhea, hypomenorrhea, menstruation delayed, and oligomenorrhea.
^2 Based on a search of the following terms: anorgasmia, delayed ejaculation, erectile dysfunction, decreased libido, loss of libido, abnormal orgasm, and sexual dysfunction.
^3 Based on a search of the following terms: breast discharge, enlargement or swelling, galactorrhea, gynecomastia, and lactation disorder.

Dose group differences with respect to prolactin elevation have been observed. In a single 8-week randomized, double-blind, fixed-dose study comparing 10 (N=199), 20 (N=200) and 40 (N=200) mg/day of oral olanzapine in adult patients with schizophrenia or schizoaffective disorder, incidence of prolactin elevation >24.2 ng/mL (female) or >18.77 ng/mL (male) at any time during the trial (10 mg/day: 31.2%; 20 mg/day: 42.7%; 40 mg/day: 61.1%) indicated significant differences between 10 vs 40 mg/day and 20 vs 40 mg/day.

5.16 Use in Combination with Fluoxetine, Lithium, or Valproate

When using ZYPREXA and fluoxetine in combination, the prescriber should also refer to the Warnings and Precautions section of the package insert for Symbyax. When using ZYPREXA in combination with lithium or valproate, the prescriber should refer to the Warnings and Precautions sections of the package inserts for lithium or valproate [see Drug Interactions (7)].

5.17 Laboratory Tests

Fasting blood glucose testing and lipid profile at the beginning of, and periodically during, treatment is recommended [see Warnings and Precautions (5.5) and Patient Counseling Information (17)].

6 ADVERSE REACTIONS

When using ZYPREXA and fluoxetine in combination, also refer to the Adverse Reactions section of the package insert for Symbyax.

6.1 Clinical Trials Experience

Because clinical trials are conducted under widely varying conditions, adverse reaction rates observed in the clinical trials of a drug cannot be directly compared to rates in the clinical trials of another drug and may not reflect or predict the rates observed in practice.

Clinical Trials in Adults

The information below for olanzapine is derived from a clinical trial database for olanzapine consisting of 10,504 adult patients with approximately 4765 patient-years of exposure to olanzapine plus 722 patients with exposure to intramuscular olanzapine for injection. This database includes: (1) 2500 patients who participated in multiple-dose oral olanzapine premarketing trials in schizophrenia and Alzheimer's disease representing approximately 1122 patient-years of exposure as of February 14, 1995; (2) 182 patients who participated in oral olanzapine premarketing bipolar I disorder (manic or mixed episodes) trials representing approximately 66 patient-years of exposure; (3) 191 patients who participated in an oral olanzapine trial of patients having various psychiatric symptoms in association with Alzheimer's disease representing approximately 29 patient-years of exposure; (4) 5788 additional patients from 88 oral olanzapine clinical trials as of December 31, 2001; (5) 1843 additional patients from 41 olanzapine clinical trials as of October 31, 2011; and (6) 722 patients who participated in intramuscular olanzapine for injection premarketing trials in agitated patients with schizophrenia, bipolar I disorder (manic or mixed episodes), or dementia. Also included below is information from the premarketing 6-week clinical study database for olanzapine in combination with lithium or valproate, consisting of 224 patients who participated in bipolar I disorder (manic or mixed episodes) trials with approximately 22 patient-years of exposure.

The conditions and duration of treatment with olanzapine varied greatly and included (in overlapping categories) open-label and double-blind phases of studies, inpatients and outpatients, fixed-dose and dose-titration studies, and short-term or longer-term exposure. Adverse reactions were assessed by collecting adverse reactions, results of physical examinations, vital signs, weights, laboratory analytes, ECGs, chest x-rays, and results of ophthalmologic examinations.

Certain portions of the discussion below relating to objective or numeric safety parameters, namely, dose-dependent adverse reactions, vital sign changes, weight gain, laboratory changes, and ECG changes are derived from studies in patients with schizophrenia and have not been duplicated for bipolar I disorder (manic or mixed episodes) or agitation. However, this information is also generally applicable to bipolar I disorder (manic or mixed episodes) and agitation.

Adverse reactions during exposure were obtained by spontaneous report and recorded by clinical investigators using terminology of their own choosing. Consequently, it is not possible to provide a meaningful estimate of the proportion of individuals experiencing adverse reactions without first grouping similar types of reactions into a smaller number of standardized reaction categories. In the tables and tabulations that follow, MedDRA and COSTART Dictionary terminology has been used to classify reported adverse reactions.

The stated frequencies of adverse reactions represent the proportion of individuals who experienced, at least once, a treatment-emergent adverse reaction of the type listed. A reaction was considered treatment emergent if it occurred for the first time or worsened while receiving therapy following baseline evaluation. The reported reactions do not include those reaction terms that were so general as to be uninformative. Reactions listed elsewhere in labeling may not be repeated below. It is important to emphasize that, although the reactions occurred during treatment with olanzapine, they were not necessarily caused by it. The entire label should be read to gain a complete understanding of the safety profile of olanzapine.

The prescriber should be aware that the figures in the tables and tabulations cannot be used to predict the incidence of side effects in the course of usual medical practice where patient characteristics and other factors differ from those that prevailed in the clinical trials. Similarly, the cited frequencies cannot be compared with figures obtained from other clinical investigations involving different treatments, uses, and investigators. The cited figures, however, do provide the prescribing healthcare provider with some basis for estimating the relative contribution of drug and nondrug factors to the adverse reactions incidence in the population studied.

Incidence of Adverse Reactions in Short-Term, Placebo-Controlled and Combination Trials

The following findings are based on premarketing trials of (1) oral olanzapine for schizophrenia, bipolar I disorder (manic or mixed episodes), a subsequent trial of patients having various psychiatric symptoms in association with Alzheimer's disease, and premarketing combination trials, and (2) intramuscular olanzapine for injection in agitated patients with schizophrenia or bipolar I mania.

Adverse Reactions Associated with Discontinuation of Treatment in Short-Term, Placebo-Controlled Trials

Schizophrenia — Overall, there was no difference in the incidence of discontinuation due to adverse reactions (5% for oral olanzapine vs 6% for placebo). However, discontinuations due to increases in ALT were considered to be drug related (2% for oral olanzapine vs 0% for placebo).

Bipolar I Disorder (Manic or Mixed Episodes) Monotherapy — Overall, there was no difference in the incidence of discontinuation due to adverse reactions (2% for oral olanzapine vs 2% for placebo).

Agitation — Overall, there was no difference in the incidence of discontinuation due to adverse reactions (0.4% for intramuscular olanzapine for injection vs 0% for placebo).

Adverse Reactions Associated with Discontinuation of Treatment in Short-Term Combination Trials

Bipolar I Disorder (Manic or Mixed Episodes), Olanzapine as Adjunct to Lithium or Valproate — In a study of patients who were already tolerating either lithium or valproate as monotherapy, discontinuation rates due to adverse reactions were 11% for the combination of oral olanzapine with lithium or valproate compared to 2% for patients who remained on lithium or valproate monotherapy. Discontinuations with the combination of oral olanzapine and lithium or valproate that occurred in more than 1 patient were: somnolence (3%), weight gain (1%), and peripheral edema (1%).

Commonly Observed Adverse Reactions in Short-Term, Placebo-Controlled Trials

The most commonly observed adverse reactions associated with the use of oral olanzapine (incidence of 5% or greater) and not observed at an equivalent incidence among placebo-treated patients (olanzapine incidence at least twice that for placebo) were:

Table 9: Common Treatment-Emergent Adverse Reactions Associated with the Use of Oral Olanzapine in 6-Week Trials — SCHIZOPHRENIA
Adverse Reaction | Percentage of Patients Reporting Event
Adverse Reaction | Olanzapine (N=248) | Placebo (N=118)
Postural hypotension | 5 | 2
Constipation | 9 | 3
Weight gain | 6 | 1
Dizziness | 11 | 4
Personality disordera | 8 | 4
Akathisia | 5 | 1
a Personality disorder is the COSTART term for designating nonaggressive objectionable behavior.

Table 10: Common Treatment-Emergent Adverse Reactions Associated with the Use of Oral Olanzapine in 3-Week and 4-Week Trials — Bipolar I Disorder (Manic or Mixed Episodes)
Adverse Reaction | Percentage of Patients Reporting Event
Adverse Reaction | Olanzapine (N=125) | Placebo (N=129)
Asthenia | 15 | 6
Dry mouth | 22 | 7
Constipation | 11 | 5
Dyspepsia | 11 | 5
Increased appetite | 6 | 3
Somnolence | 35 | 13
Dizziness | 18 | 6
Tremor | 6 | 3

Olanzapine Intramuscular — There was 1 adverse reaction (somnolence) observed at an incidence of 5% or greater among intramuscular olanzapine for injection-treated patients and not observed at an equivalent incidence among placebo-treated patients (olanzapine incidence at least twice that for placebo) during the placebo-controlled premarketing studies. The incidence of somnolence during the 24 hour IM treatment period in clinical trials in agitated patients with schizophrenia or bipolar I mania was 6% for intramuscular olanzapine for injection and 3% for placebo.

Adverse Reactions Occurring at an Incidence of 2% or More among Oral Olanzapine-Treated Patients in Short-Term, Placebo-Controlled Trials

Table 11 enumerates the incidence, rounded to the nearest percent, of treatment-emergent adverse reactions that occurred in 2% or more of patients treated with oral olanzapine (doses ≥2.5 mg/day) and with incidence greater than placebo who participated in the acute phase of placebo-controlled trials.

Table 11: Treatment-Emergent Adverse Reactions: Incidence in Short-Term, Placebo-Controlled Clinical Trials with Oral Olanzapine
Body System/Adverse Reaction | Percentage of Patients Reporting Event
Body System/Adverse Reaction | Olanzapine (N=532) | Placebo (N=294)
Body as a Whole
Accidental injury | 12 | 8
Asthenia | 10 | 9
Fever | 6 | 2
Back pain | 5 | 2
Chest pain | 3 | 1
Cardiovascular System
Postural hypotension | 3 | 1
Tachycardia | 3 | 1
Hypertension | 2 | 1
Digestive System
Dry mouth | 9 | 5
Constipation | 9 | 4
Dyspepsia | 7 | 5
Vomiting | 4 | 3
Increased appetite | 3 | 2
Hemic and Lymphatic System
Ecchymosis | 5 | 3
Metabolic and Nutritional Disorders
Weight gain | 5 | 3
Peripheral edema | 3 | 1
Musculoskeletal System
Extremity pain (other than joint) | 5 | 3
Joint pain | 5 | 3
Nervous System
Somnolence | 29 | 13
Insomnia | 12 | 11
Dizziness | 11 | 4
Abnormal gait | 6 | 1
Tremor | 4 | 3
Akathisia | 3 | 2
Hypertonia | 3 | 2
Articulation impairment | 2 | 1
Respiratory System
Rhinitis | 7 | 6
Cough increased | 6 | 3
Pharyngitis | 4 | 3
Special Senses
Amblyopia | 3 | 2
Urogenital System
Urinary incontinence | 2 | 1
Urinary tract infection | 2 | 1

Dose Dependency of Adverse Reactions

A dose group difference has been observed for fatigue, dizziness, weight gain and prolactin elevation. In a single 8-week randomized, double-blind, fixed-dose study comparing 10 (N=199), 20 (N=200) and 40 (N=200) mg/day of oral olanzapine in adult patients with schizophrenia or schizoaffective disorder, incidence of fatigue (10 mg/day: 1.5%; 20 mg/day: 2.1%; 40 mg/day: 6.6%) was observed with significant differences between 10 vs 40 and 20 vs 40 mg/day. The incidence of dizziness (10 mg/day: 2.6%; 20 mg/day: 1.6%; 40 mg/day: 6.6%) was observed with significant differences between 20 vs 40 mg. Dose group differences were also noted for weight gain and prolactin elevation [see Warnings and Precautions (5.5, 5.15)].

The following table addresses dose relatedness for other adverse reactions using data from a schizophrenia trial involving fixed dosage ranges of oral olanzapine. It enumerates the percentage of patients with treatment-emergent adverse reactions for the 3 fixed-dose range groups and placebo. The data were analyzed using the Cochran-Armitage test, excluding the placebo group, and the table includes only those adverse reactions for which there was a trend.

Table 12: Percentage of Patients from a Schizophrenia Trial with Treatment-Emergent Adverse Reactions for the 3 Dose Range Groups and Placebo
 | Percentage of Patients Reporting Event
 |  | Olanzapine | Olanzapine | Olanzapine
 | Placebo | 5 ± 2.5 mg/day | 10 ± 2.5 mg/day | 15 ± 2.5 mg/day
Adverse Reaction | (N=68) | (N=65) | (N=64) | (N=69)
Asthenia | 15 | 8 | 9 | 20
Dry mouth | 4 | 3 | 5 | 13
Nausea | 9 | 0 | 2 | 9
Somnolence | 16 | 20 | 30 | 39
Tremor | 3 | 0 | 5 | 7

Commonly Observed Adverse Reactions in Short-Term Trials of Oral Olanzapine as Adjunct to Lithium or Valproate

In the bipolar I disorder (manic or mixed episodes) adjunct placebo-controlled trials, the most commonly observed adverse reactions associated with the combination of olanzapine and lithium or valproate (incidence of ≥5% and at least twice placebo) were:

Table 13: Common Treatment-Emergent Adverse Reactions Associated with the Use of Oral Olanzapine in 6-Week Adjunct to Lithium or Valproate Trials — Bipolar I Disorder (Manic or Mixed Episodes)
Adverse Reaction | Percentage of Patients Reporting Event
Adverse Reaction | Olanzapine with lithium or valproate (N=229) | Placebo with lithium or valproate (N=115)
Dry mouth | 32 | 9
Weight gain | 26 | 7
Increased appetite | 24 | 8
Dizziness | 14 | 7
Back pain | 8 | 4
Constipation | 8 | 4
Speech disorder | 7 | 1
Increased salivation | 6 | 2
Amnesia | 5 | 2
Paresthesia | 5 | 2

Adverse Reactions Occurring at an Incidence of 2% or More among Oral Olanzapine-Treated Patients in Short-Term Trials of Olanzapine as Adjunct to Lithium or Valproate

Table 14 enumerates the incidence, rounded to the nearest percent, of treatment-emergent adverse reactions that occurred in 2% or more of patients treated with the combination of olanzapine (doses ≥5 mg/day) and lithium or valproate and with incidence greater than lithium or valproate alone who participated in the acute phase of placebo-controlled combination trials.

Table 14: Treatment-Emergent Adverse Reactions: Incidence in Short-Term, Placebo-Controlled Clinical Trials of Oral Olanzapine as Adjunct to Lithium or Valproate
Body System/Adverse Reaction | Percentage of Patients Reporting Event
Body System/Adverse Reaction | Olanzapine with lithium or valproate (N=229) | Placebo with lithium or valproate (N=115)
Body as a Whole
Asthenia | 18 | 13
Back pain | 8 | 4
Accidental injury | 4 | 2
Chest pain | 3 | 2
Cardiovascular System
Hypertension | 2 | 1
Digestive System
Dry mouth | 32 | 9
Increased appetite | 24 | 8
Thirst | 10 | 6
Constipation | 8 | 4
Increased salivation | 6 | 2
Metabolic and Nutritional Disorders
Weight gain | 26 | 7
Peripheral edema | 6 | 4
Edema | 2 | 1
Nervous System
Somnolence | 52 | 27
Tremor | 23 | 13
Depression | 18 | 17
Dizziness | 14 | 7
Speech disorder | 7 | 1
Amnesia | 5 | 2
Paresthesia | 5 | 2
Apathy | 4 | 3
Confusion | 4 | 1
Euphoria | 3 | 2
Incoordination | 2 | 0
Respiratory System
Pharyngitis | 4 | 1
Dyspnea | 3 | 1
Skin and Appendages
Sweating | 3 | 1
Acne | 2 | 0
Dry skin | 2 | 0
Special Senses
Amblyopia | 9 | 5
Abnormal vision | 2 | 0
Urogenital System
Dysmenorrheaa | 2 | 0
Vaginitisa | 2 | 0
a Denominator used was for females only (olanzapine, N=128; placebo, N=51).

For specific information about the adverse reactions observed with lithium or valproate, refer to the Adverse Reactions section of the package inserts for these other products.

Adverse Reactions Occurring at an Incidence of 1% or More among Intramuscular Olanzapine for Injection-Treated Patients in Short-Term, Placebo-Controlled Trials

Table 15 enumerates the incidence, rounded to the nearest percent, of treatment-emergent adverse reactions that occurred in 1% or more of patients treated with intramuscular olanzapine for injection (dose range of 2.5-10 mg/injection) and with incidence greater than placebo who participated in the short-term, placebo-controlled trials in agitated patients with schizophrenia or bipolar I mania.

Table 15: Treatment-Emergent Adverse Reactions: Incidence in Short-Term (24 Hour), Placebo-Controlled Clinical Trials with Intramuscular Olanzapine for Injection in Agitated Patients with Schizophrenia or Bipolar I Mania
Body System/Adverse Reaction | Percentage of Patients Reporting Event
Body System/Adverse Reaction | Olanzapine (N=415) | Placebo (N=150)
Body as a Whole
Asthenia | 2 | 1
Cardiovascular System
Hypotension | 2 | 0
Postural hypotension | 1 | 0
Nervous System
Somnolence | 6 | 3
Dizziness | 4 | 2
Tremor | 1 | 0

Extrapyramidal Symptoms

The following table enumerates the percentage of patients with treatment-emergent extrapyramidal symptoms as assessed by categorical analyses of formal rating scales during acute therapy in a controlled clinical trial comparing oral olanzapine at 3 fixed doses with placebo in the treatment of schizophrenia in a 6-week trial.

Table 16: Treatment-Emergent Extrapyramidal Symptoms Assessed by Rating Scales Incidence in a Fixed Dosage Range, Placebo-Controlled Clinical Trial of Oral Olanzapine in Schizophrenia — Acute Phase
 | Percentage of Patients Reporting Event
 | Placebo | Olanzapine 5 ± 2.5 mg/day | Olanzapine 10 ± 2.5 mg/day | Olanzapine 15 ± 2.5 mg/day
Parkinsonisma | 15 | 14 | 12 | 14
Akathisiab | 23 | 16 | 19 | 27
a Percentage of patients with a Simpson-Angus Scale total score >3.
b Percentage of patients with a Barnes Akathisia Scale global score ≥2.

The following table enumerates the percentage of patients with treatment-emergent extrapyramidal symptoms as assessed by spontaneously reported adverse reactions during acute therapy in the same controlled clinical trial comparing olanzapine at 3 fixed doses with placebo in the treatment of schizophrenia in a 6-week trial.

Table 17: Treatment-Emergent Extrapyramidal Symptoms Assessed by Adverse Reactions Incidence in a Fixed Dosage Range, Placebo-Controlled Clinical Trial of Oral Olanzapine in Schizophrenia — Acute Phase
 | Percentage of Patients Reporting Event
 | Placebo (N=68) | Olanzapine 5 ± 2.5 mg/day (N=65) | Olanzapine 10 ± 2.5 mg/day (N=64) | Olanzapine 15 ± 2.5 mg/day (N=69)
Dystonic eventsa | 1 | 3 | 2 | 3
Parkinsonism eventsb | 10 | 8 | 14 | 20
Akathisia eventsc | 1 | 5 | 11 | 10
Dyskinetic eventsd | 4 | 0 | 2 | 1
Residual eventse | 1 | 2 | 5 | 1
Any extrapyramidal event | 16 | 15 | 25 | 32
a Patients with the following COSTART terms were counted in this category: dystonia, generalized spasm, neck rigidity, oculogyric crisis, opisthotonos, torticollis.
b Patients with the following COSTART terms were counted in this category: akinesia, cogwheel rigidity, extrapyramidal syndrome, hypertonia, hypokinesia, masked facies, tremor.
c Patients with the following COSTART terms were counted in this category: akathisia, hyperkinesia.
d Patients with the following COSTART terms were counted in this category: buccoglossal syndrome, choreoathetosis, dyskinesia, tardive dyskinesia.
e Patients with the following COSTART terms were counted in this category: movement disorder, myoclonus, twitching.

The following table enumerates the percentage of adolescent patients with treatment-emergent extrapyramidal symptoms as assessed by spontaneously reported adverse reactions during acute therapy (dose range: 2.5 to 20 mg/day).

Table 18: Treatment-Emergent Extrapyramidal Symptoms Assessed by Adverse Reactions Incidence in Placebo-Controlled Clinical Trials of Oral Olanzapine in Schizophrenia and Bipolar I Disorder — Adolescents
 | Percentage of Patients Reporting Event
 | Placebo | Olanzapine
Categoriesa | (N=89) | (N=179)
Dystonic events | 0 | 1
Parkinsonism events | 2 | 1
Akathisia events | 4 | 6
Dyskinetic events | 0 | 1
Nonspecific events | 0 | 4
Any extrapyramidal event | 6 | 10
a Categories are based on Standard MedDRA Queries (SMQ) for extrapyramidal symptoms as defined in MedDRA version 12.0.

The following table enumerates the percentage of patients with treatment-emergent extrapyramidal symptoms as assessed by categorical analyses of formal rating scales during controlled clinical trials comparing fixed doses of intramuscular olanzapine for injection with placebo in agitation. Patients in each dose group could receive up to 3 injections during the trials [see Clinical Studies (14.3)]. Patient assessments were conducted during the 24 hours following the initial dose of intramuscular olanzapine for injection.

Table 19: Treatment-Emergent Extrapyramidal Symptoms Assessed by Rating Scales Incidence in a Fixed Dose, Placebo-Controlled Clinical Trial of Intramuscular Olanzapine for Injection in Agitated Patients with Schizophrenia
 | Percentage of Patients Reporting Event
 | Placebo | Olanzapine IM 2.5 mg | Olanzapine IM 5 mg | Olanzapine IM 7.5 mg | Olanzapine IM 10 mg
Parkinsonisma | 0 | 0 | 0 | 0 | 3
Akathisiab | 0 | 0 | 5 | 0 | 0
a Percentage of patients with a Simpson-Angus Scale total score >3.
b Percentage of patients with a Barnes Akathisia Scale global score ≥2.

The following table enumerates the percentage of patients with treatment-emergent extrapyramidal symptoms as assessed by spontaneously reported adverse reactions in the same controlled clinical trial comparing fixed doses of intramuscular olanzapine for injection with placebo in agitated patients with schizophrenia.

Table 20: Treatment-Emergent Extrapyramidal Symptoms Assessed by Adverse Reactions Incidence in a Fixed Dose, Placebo-Controlled Clinical Trial of Intramuscular Olanzapine for Injection in Agitated Patients with Schizophrenia
 | Percentage of Patients Reporting Event
 | Placebo (N=45) | Olanzapine IM 2.5 mg (N=48) | Olanzapine IM 5 mg (N=45) | Olanzapine IM 7.5 mg (N=46) | Olanzapine IM 10 mg (N=46)
Dystonic eventsa | 0 | 0 | 0 | 0 | 0
Parkinsonism eventsb | 0 | 4 | 2 | 0 | 0
Akathisia eventsc | 0 | 2 | 0 | 0 | 0
Dyskinetic eventsd | 0 | 0 | 0 | 0 | 0
Residual eventse | 0 | 0 | 0 | 0 | 0
Any extrapyramidal events | 0 | 4 | 2 | 0 | 0
a Patients with the following COSTART terms were counted in this category: dystonia, generalized spasm, neck rigidity, oculogyric crisis, opisthotonos, torticollis.
b Patients with the following COSTART terms were counted in this category: akinesia, cogwheel rigidity, extrapyramidal syndrome, hypertonia, hypokinesia, masked facies, tremor.
c Patients with the following COSTART terms were counted in this category: akathisia, hyperkinesia.
d Patients with the following COSTART terms were counted in this category: buccoglossal syndrome, choreoathetosis, dyskinesia, tardive dyskinesia.
e Patients with the following COSTART terms were counted in this category: movement disorder, myoclonus, twitching.

Dystonia, Class Effect: Symptoms of dystonia, prolonged abnormal contractions of muscle groups, may occur in susceptible individuals during the first few days of treatment. Dystonic symptoms include: spasm of the neck muscles, sometimes progressing to tightness of the throat, swallowing difficulty, difficulty breathing, and/or protrusion of the tongue. While these symptoms can occur at low doses, the frequency and severity are greater with high potency and at higher doses of first generation antipsychotic drugs. In general, an elevated risk of acute dystonia may be observed in males and younger age groups receiving antipsychotics; however, events of dystonia have been reported infrequently (<1%) with olanzapine use.

Other Adverse Reactions

Other Adverse Reactions Observed During the Clinical Trial Evaluation of Oral Olanzapine

Following is a list of treatment-emergent adverse reactions reported by patients treated with oral olanzapine (at multiple doses ≥1 mg/day) in clinical trials. This listing is not intended to include reactions (1) already listed in previous tables or elsewhere in labeling, (2) for which a drug cause was remote, (3) which were so general as to be uninformative, (4) which were not considered to have significant clinical implications, or (5) which occurred at a rate equal to or less than placebo. Reactions are classified by body system using the following definitions: frequent adverse reactions are those occurring in at least 1/100 patients; infrequent adverse reactions are those occurring in 1/100 to 1/1000 patients; rare reactions are those occurring in fewer than 1/1000 patients.

Body as a Whole — Infrequent: chills, face edema, photosensitivity reaction, suicide attempt^1; Rare: chills and fever, hangover effect, sudden death^1.Cardiovascular System — Infrequent: cerebrovascular accident, vasodilatation.Digestive System — Infrequent: abdominal distension, nausea and vomiting, tongue edema; Rare: ileus, intestinal obstruction, liver fatty deposit.Hemic and Lymphatic System — Infrequent: thrombocytopenia.Metabolic and Nutritional Disorders — Frequent: alkaline phosphatase increased; Infrequent: bilirubinemia, hypoproteinemia.Musculoskeletal System — Rare: osteoporosis.Nervous System — Infrequent: ataxia, dysarthria, libido decreased, stupor; Rare: coma.Respiratory System — Infrequent: epistaxis; Rare: lung edema.Skin and Appendages — Infrequent: alopecia.Special Senses — Infrequent: abnormality of accommodation, dry eyes; Rare: mydriasis.Urogenital System — Infrequent: amenorrhea^2, breast pain, decreased menstruation, impotence^2, increased menstruation^2, menorrhagia^2, metrorrhagia^2, polyuria^2, urinary frequency, urinary retention, urinary urgency, urination impaired.

^1 These terms represent serious adverse events but do not meet the definition for adverse drug reactions. They are included here because of their seriousness.

^2 Adjusted for gender.

Other Adverse Reactions Observed During the Clinical Trial Evaluation of Intramuscular Olanzapine for Injection

Following is a list of treatment-emergent adverse reactions reported by patients treated with intramuscular olanzapine for injection (at 1 or more doses ≥2.5 mg/injection) in clinical trials. This listing is not intended to include reactions (1) already listed in previous tables or elsewhere in labeling, (2) for which a drug cause was remote, (3) which were so general as to be uninformative, (4) which were not considered to have significant clinical implications, or (5) for which occurred at a rate equal to or less than placebo. Reactions are classified by body system using the following definitions: frequent adverse reactions are those occurring in at least 1/100 patients; infrequent adverse reactions are those occurring in 1/100 to 1/1000 patients.

Body as a Whole — Frequent: injection site pain.Cardiovascular System — Infrequent: syncope.Digestive System — Infrequent: nausea.Metabolic and Nutritional Disorders — Infrequent:creatine phosphokinase increased.

Clinical Trials in Adolescent Patients (age 13 to 17 years)

Commonly Observed Adverse Reactions in Oral Olanzapine Short-Term, Placebo-Controlled Trials

Adverse reactions in adolescent patients treated with oral olanzapine (doses ≥2.5 mg) reported with an incidence of 5% or more and reported at least twice as frequently as placebo-treated patients are listed in Table 21.

Table 21: Treatment-Emergent Adverse Reactions of ≥5% Incidence among Adolescents (13-17 Years Old) with Schizophrenia or Bipolar I Disorder (Manic or Mixed Episodes)
Adverse Reactions | Percentage of Patients Reporting Event
Adverse Reactions | 6 Week Trial % Schizophrenia Patients |  | 3 Week Trial % Bipolar Patients
Adverse Reactions | Olanzapine (N=72) | Placebo (N=35) | Olanzapine (N=107) | Placebo (N=54)
Sedationa | 39 | 9 | 48 | 9
Weight increased | 31 | 9 | 29 | 4
Headache | 17 | 6 | 17 | 17
Increased appetite | 17 | 9 | 29 | 4
Dizziness | 8 | 3 | 7 | 2
Abdominal painb | 6 | 3 | 6 | 7
Pain in extremity | 6 | 3 | 5 | 0
Fatigue | 3 | 3 | 14 | 6
Dry mouth | 4 | 0 | 7 | 0
a Patients with the following MedDRA terms were counted in this category: hypersomnia, lethargy, sedation, somnolence.
b Patients with the following MedDRA terms were counted in this category: abdominal pain, abdominal pain lower, abdominal pain upper.

Adverse Reactions Occurring at an Incidence of 2% or More among Oral Olanzapine-Treated Patients in Short-Term (3-6 weeks), Placebo-Controlled Trials

Adverse reactions in adolescent patients treated with oral olanzapine (doses ≥2.5 mg) reported with an incidence of 2% or more and greater than placebo are listed in Table 22.

Table 22: Treatment-Emergent Adverse Reactions of ≥2% Incidence among Adolescents (13-17 Years Old) (Combined Incidence from Short-Term, Placebo-Controlled Clinical Trials of Schizophrenia or Bipolar I Disorder [Manic or Mixed Episodes])
Adverse Reaction | Percentage of Patients Reporting Event
Adverse Reaction | Olanzapine (N=179) | Placebo (N=89)
Sedationa | 44 | 9
Weight increased | 30 | 6
Increased appetite | 24 | 6
Headache | 17 | 12
Fatigue | 9 | 4
Dizziness | 7 | 2
Dry mouth | 6 | 0
Pain in extremity | 5 | 1
Constipation | 4 | 0
Nasopharyngitis | 4 | 2
Diarrhea | 3 | 0
Restlessness | 3 | 2
Liver enzymes increasedb | 8 | 1
Dyspepsia | 3 | 1
Epistaxis | 3 | 0
Respiratory tract infectionc | 3 | 2
Sinusitis | 3 | 0
Arthralgia | 2 | 0
Musculoskeletal stiffness | 2 | 0
a Patients with the following MedDRA terms were counted in this category: hypersomnia, lethargy, sedation, somnolence.
b The terms alanine aminotransferase (ALT), aspartate aminotransferase (AST), and hepatic enzyme were combined under liver enzymes.
c Patients with the following MedDRA terms were counted in this category: lower respiratory tract infection, respiratory tract infection, respiratory tract infection viral, upper respiratory tract infection, viral upper respiratory tract infection.

Vital Signs and Laboratory Studies

Vital Sign Changes — Oral olanzapine was associated with orthostatic hypotension and tachycardia in clinical trials. Intramuscular olanzapine for injection was associated with bradycardia, hypotension, and tachycardia in clinical trials [see Warnings and Precautions (5)].

Laboratory Changes

Olanzapine Monotherapy in Adults: An assessment of the premarketing experience for olanzapine revealed an association with asymptomatic increases in ALT, AST, and GGT. Within the original premarketing database of about 2400 adult patients with baseline ALT ≤90 IU/L, the incidence of ALT elevations to >200 IU/L was 2% (50/2381). None of these patients experienced jaundice or other symptoms attributable to liver impairment and most had transient changes that tended to normalize while olanzapine treatment was continued.

In placebo-controlled olanzapine monotherapy studies in adults, clinically significant ALT elevations (change from <3 times the upper limit of normal [ULN] at baseline to ≥3 times ULN) were observed in 5% (77/1426) of patients exposed to olanzapine compared to 1% (10/1187) of patients exposed to placebo. ALT elevations ≥5 times ULN were observed in 2% (29/1438) of olanzapine-treated patients, compared to 0.3% (4/1196) of placebo-treated patients. ALT values returned to normal, or were decreasing, at last follow-up in the majority of patients who either continued treatment with olanzapine or discontinued olanzapine. No patient with elevated ALT values experienced jaundice, liver failure, or met the criteria for Hy's Rule.

From an analysis of the laboratory data in an integrated database of 41 completed clinical studies in adult patients treated with oral olanzapine, high GGT levels were recorded in ≥1% (88/5245) of patients.

Caution should be exercised in patients with signs and symptoms of hepatic impairment, in patients with pre-existing conditions associated with limited hepatic functional reserve, and in patients who are being treated with potentially hepatotoxic drugs.

Olanzapine administration was also associated with increases in serum prolactin [see Warnings and Precautions (5.15)], with an asymptomatic elevation of the eosinophil count in 0.3% of patients, and with an increase in CPK.

From an analysis of the laboratory data in an integrated database of 41 completed clinical studies in adult patients treated with oral olanzapine, elevated uric acid was recorded in ≥3% (171/4641) of patients.

Olanzapine Monotherapy in Adolescents: In placebo-controlled clinical trials of adolescent patients with schizophrenia or bipolar I disorder (manic or mixed episodes), greater frequencies for the following treatment-emergent findings, at anytime, were observed in laboratory analytes compared to placebo: elevated ALT (≥3X ULN in patients with ALT at baseline <3X ULN), (12% vs 2%); elevated AST (28% vs 4%); low total bilirubin (22% vs 7%); elevated GGT (10% vs 1%); and elevated prolactin (47% vs 7%).

In placebo-controlled olanzapine monotherapy studies in adolescents, clinically significant ALT elevations (change from <3 times ULN at baseline to ≥3 times ULN) were observed in 12% (22/192) of patients exposed to olanzapine compared to 2% (2/109) of patients exposed to placebo. ALT elevations ≥5 times ULN were observed in 4% (8/192) of olanzapine-treated patients, compared to 1% (1/109) of placebo-treated patients. ALT values returned to normal, or were decreasing, at last follow-up in the majority of patients who either continued treatment with olanzapine or discontinued olanzapine. No adolescent patient with elevated ALT values experienced jaundice, liver failure, or met the criteria for Hy's Rule.

ECG Changes — In pooled studies of adults as well as pooled studies of adolescents, there were no significant differences between olanzapine and placebo in the proportions of patients experiencing potentially important changes in ECG parameters, including QT, QTc (Fridericia corrected), and PR intervals. Olanzapine use was associated with a mean increase in heart rate compared to placebo (adults: +2.4 beats per minute vs no change with placebo; adolescents: +6.3 beats per minute vs -5.1 beats per minute with placebo). This increase in heart rate may be related to olanzapine's potential for inducing orthostatic changes [see Warnings and Precautions (5.7)].

6.2 Postmarketing Experience

The following adverse reactions have been identified during post-approval use of ZYPREXA. Because these reactions are reported voluntarily from a population of uncertain size, it is difficult to reliably estimate their frequency or evaluate a causal relationship to drug exposure.

Adverse reactions reported since market introduction that were temporally (but not necessarily causally) related to ZYPREXA therapy include the following: allergic reaction (e.g., anaphylactoid reaction, angioedema, pruritus or urticaria), cholestatic or mixed liver injury, diabetic coma, diabetic ketoacidosis, discontinuation reaction (diaphoresis, nausea or vomiting), drug reaction with eosinophilia and systemic symptoms (DRESS), hepatitis, jaundice, neutropenia, pancreatitis, priapism, rash, restless legs syndrome, rhabdomyolysis, salivary hypersecretion, stuttering^1, venous thromboembolic events (including pulmonary embolism and deep venous thrombosis), fecal incontinence, somnambulism, and syndrome of inappropriate antidiuretic hormone secretion (SIADH). Random cholesterol levels of ≥240 mg/dL and random triglyceride levels of ≥1000 mg/dL have been reported.

^1 Stuttering was only studied in oral and long acting injection (LAI) formulations.

7 DRUG INTERACTIONS

The risks of using olanzapine in combination with other drugs have not been extensively evaluated in systematic studies.

7.1 Potential for Other Drugs to Affect Olanzapine

Diazepam — The co-administration of diazepam with olanzapine potentiated the orthostatic hypotension observed with olanzapine [see Drug Interactions (7.2)].

Cimetidine and Antacids — Single doses of cimetidine (800 mg) or aluminum- and magnesium-containing antacids did not affect the oral bioavailability of olanzapine.

Inducers of CYP1A2 — Carbamazepine therapy (200 mg bid) causes an approximately 50% increase in the clearance of olanzapine. This increase is likely due to the fact that carbamazepine is a potent inducer of CYP1A2 activity. Higher daily doses of carbamazepine may cause an even greater increase in olanzapine clearance.

Alcohol — Ethanol (45 mg/70 kg single dose) did not have an effect on olanzapine pharmacokinetics. The co-administration of alcohol (i.e., ethanol) with olanzapine potentiated the orthostatic hypotension observed with olanzapine [see Drug Interactions (7.2)].

Inhibitors of CYP1A2

Fluvoxamine: Fluvoxamine, a CYP1A2 inhibitor, decreases the clearance of olanzapine. This results in a mean increase in olanzapine Cmax following fluvoxamine of 54% in female nonsmokers and 77% in male smokers. The mean increase in olanzapine AUC is 52% and 108%, respectively. Lower doses of olanzapine should be considered in patients receiving concomitant treatment with fluvoxamine.

Inhibitors of CYP2D6

Fluoxetine: Fluoxetine (60 mg single dose or 60 mg daily dose for 8 days) causes a small (mean 16%) increase in the maximum concentration of olanzapine and a small (mean 16%) decrease in olanzapine clearance. The magnitude of the impact of this factor is small in comparison to the overall variability between individuals, and therefore dose modification is not routinely recommended. When using ZYPREXA and fluoxetine in combination, also refer to the Drug Interactions section of the package insert for Symbyax.

Warfarin — Warfarin (20 mg single dose) did not affect olanzapine pharmacokinetics [see Drug Interactions (7.2)].

Inducers of CYP1A2 or Glucuronyl Transferase — Omeprazole and rifampin may cause an increase in olanzapine clearance.

Charcoal — The administration of activated charcoal (1 g) reduced the Cmax and AUC of oral olanzapine by about 60%. As peak olanzapine levels are not typically obtained until about 6 hours after dosing, charcoal may be a useful treatment for olanzapine overdose.

Anticholinergic Drugs — Concomitant treatment with olanzapine and other drugs with anticholinergic activity can increase the risk for severe gastrointestinal adverse reactions related to hypomotility. ZYPREXA should be used with caution in patients receiving medications having anticholinergic (antimuscarinic) effects [see Warnings and Precautions (5.14)].

7.2 Potential for Olanzapine to Affect Other Drugs

CNS Acting Drugs — Given the primary CNS effects of olanzapine, caution should be used when olanzapine is taken in combination with other centrally acting drugs and alcohol.

Antihypertensive Agents — Olanzapine, because of its potential for inducing hypotension, may enhance the effects of certain antihypertensive agents.

Levodopa and Dopamine Agonists — Olanzapine may antagonize the effects of levodopa and dopamine agonists.

Lorazepam (IM) — Administration of intramuscular lorazepam (2 mg) 1 hour after intramuscular olanzapine for injection (5 mg) did not significantly affect the pharmacokinetics of olanzapine, unconjugated lorazepam, or total lorazepam. However, this co-administration of intramuscular lorazepam and intramuscular olanzapine for injection added to the somnolence observed with either drug alone [see Warnings and Precautions (5.7)].

Lithium — Multiple doses of olanzapine (10 mg for 8 days) did not influence the kinetics of lithium. Therefore, concomitant olanzapine administration does not require dosage adjustment of lithium [see Warnings and Precautions (5.16)].

Valproate — Olanzapine (10 mg daily for 2 weeks) did not affect the steady state plasma concentrations of valproate. Therefore, concomitant olanzapine administration does not require dosage adjustment of valproate [see Warnings and Precautions (5.16)].

Effect of Olanzapine on Drug Metabolizing Enzymes — In vitro studies utilizing human liver microsomes suggest that olanzapine has little potential to inhibit CYP1A2, CYP2C9, CYP2C19, CYP2D6, and CYP3A. Thus, olanzapine is unlikely to cause clinically important drug interactions mediated by these enzymes.

Imipramine — Single doses of olanzapine did not affect the pharmacokinetics of imipramine or its active metabolite desipramine.

Warfarin — Single doses of olanzapine did not affect the pharmacokinetics of warfarin [see Drug Interactions (7.1)].

Diazepam — Olanzapine did not influence the pharmacokinetics of diazepam or its active metabolite N-desmethyldiazepam. However, diazepam co-administered with olanzapine increased the orthostatic hypotension observed with either drug given alone [see Drug Interactions (7.1)].

Alcohol — Multiple doses of olanzapine did not influence the kinetics of ethanol [see Drug Interactions (7.1)].

Biperiden — Multiple doses of olanzapine did not influence the kinetics of biperiden.

Theophylline — Multiple doses of olanzapine did not affect the pharmacokinetics of theophylline or its metabolites.

8 USE IN SPECIFIC POPULATIONS

When using ZYPREXA and fluoxetine in combination, also refer to the Use in Specific Populations section of the package insert for Symbyax.

8.1 Pregnancy

Pregnancy Exposure Registry

There is a pregnancy exposure registry that monitors pregnancy outcomes in women exposed to atypical antipsychotics, including ZYPREXA, during pregnancy. Healthcare providers are encouraged to register patients by contacting the National Pregnancy Registry for Atypical Antipsychotics at 1-866-961-2388 or visit http://womensmentalhealth.org/clinical-and-research-programs/pregnancyregistry/.

Risk Summary

Neonates exposed to antipsychotic drugs, including ZYPREXA, during the third trimester are at risk for extrapyramidal and/or withdrawal symptoms following delivery (see Clinical Considerations). Overall available data from published epidemiologic studies of pregnant women exposed to olanzapine have not established a drug-associated risk of major birth defects, miscarriage, or adverse maternal or fetal outcomes (see Data). There are risks to the mother associated with untreated schizophrenia or bipolar I disorder and with exposure to antipsychotics, including ZYPREXA, during pregnancy (see Clinical Considerations).

Olanzapine was not teratogenic when administered orally to pregnant rats and rabbits at doses that are 9- and 30-times the daily oral maximum recommended human dose (MRHD), based on mg/m^2 body surface area; some fetal toxicities were observed at these doses (see Data).

The estimated background risk of major birth defects and miscarriage for the indicated populations is unknown. All pregnancies have a background risk of birth defects, loss, or other adverse outcomes. In the U.S. general population, the estimated background risk of major birth defects and miscarriage in clinically recognized pregnancies is 2% to 4% and 15% to 20%, respectively.

Clinical Considerations

Disease-associated maternal and embryo/fetal risk

There is a risk to the mother from untreated schizophrenia or bipolar I disorder, including increased risk of relapse, hospitalization, and suicide. Schizophrenia and bipolar I disorder are associated with increased adverse perinatal outcomes, including preterm birth. It is not known if this is a direct result of the illness or other comorbid factors.

Fetal/Neonatal adverse reactions

Extrapyramidal and/or withdrawal symptoms, including agitation, hypertonia, hypotonia, tremor, somnolence, respiratory distress, and feeding disorder have been reported in neonates who were exposed to antipsychotic drugs, including ZYPREXA, during the third trimester of pregnancy. These symptoms have varied in severity. Monitor neonates for extrapyramidal and/or withdrawal symptoms and manage symptoms appropriately. Some neonates recovered within hours or days without specific treatment; others required prolonged hospitalization.

Data

Human Data

Placental passage has been reported in published study reports; however, the placental passage ratio was highly variable ranging between 7% to 167% at birth following exposure during pregnancy. The clinical relevance of this finding is unknown.

Published data from observational studies, birth registries, and case reports that have evaluated the use of atypical antipsychotics during pregnancy do not establish an increased risk of major birth defects. A retrospective cohort study from a Medicaid database of 9258 women exposed to antipsychotics during pregnancy did not indicate an overall increased risk for major birth defects.

Animal Data

In oral reproduction studies in rats at doses up to 18 mg/kg/day and in rabbits at doses up to 30 mg/kg/day (9 and 30 times the daily oral MRHD based on mg/m^2 body surface area, respectively), no evidence of teratogenicity was observed. In an oral rat teratology study, early resorptions and increased numbers of nonviable fetuses were observed at a dose of 18 mg/kg/day (9 times the daily oral MRHD based on mg/m^2 body surface area), and gestation was prolonged at 10 mg/kg/day (5 times the daily oral MRHD based on mg/m^2 body surface area). In an oral rabbit teratology study, fetal toxicity manifested as increased resorptions and decreased fetal weight, occurred at a maternally toxic dose of 30 mg/kg/day (30 times the daily oral MRHD based on mg/m^2 body surface area).

8.2 Lactation

Risk Summary

Olanzapine is present in human milk. There are reports of excess sedation, irritability, poor feeding and extrapyramidal symptoms (tremors and abnormal muscle movements) in infants exposed to olanzapine through breast milk (see Clinical Considerations). There is no information on the effects of olanzapine on milk production.

The developmental and health benefits of breastfeeding should be considered along with the mother's clinical need for ZYPREXA and any potential adverse effects on the breastfed child from ZYPREXA or from the mother's underlying condition.

Clinical Considerations

Infants exposed to ZYPREXA should be monitored for excess sedation, irritability, poor feeding, and extrapyramidal symptoms (tremors and abnormal muscle movements).

8.3 Females and Males of Reproductive Potential

Infertility

Females

Based on the pharmacologic action of olanzapine (D2 receptor antagonism), treatment with ZYPREXA may result in an increase in serum prolactin levels, which may lead to a reversible reduction in fertility in females of reproductive potential [see Warnings and Precautions (5.15)].

8.4 Pediatric Use

The safety and effectiveness of oral ZYPREXA in the treatment of schizophrenia and manic or mixed episodes associated with bipolar I disorder were established in short-term studies in adolescents (ages 13 to 17 years). Use of ZYPREXA in adolescents is supported by evidence from adequate and well-controlled studies of ZYPREXA in which 268 adolescents received ZYPREXA in a range of 2.5 to 20 mg/day [see Clinical Studies (14.1, 14.2)]. Recommended starting dose for adolescents is lower than that for adults [see Dosage and Administration (2.1, 2.2)]. Compared to patients from adult clinical trials, adolescents were likely to gain more weight, experience increased sedation, and have greater increases in total cholesterol, triglycerides, LDL cholesterol, prolactin and hepatic aminotransferase levels [see Warnings and Precautions (5.5, 5.15, 5.17) and Adverse Reactions (6.1)]. When deciding among the alternative treatments available for adolescents, clinicians should consider the increased potential (in adolescents as compared with adults) for weight gain and dyslipidemia. Clinicians should consider the potential long-term risks when prescribing to adolescents, and in many cases this may lead them to consider prescribing other drugs first in adolescents [see Indications and Usage (1.1, 1.2)].

Safety and effectiveness of olanzapine in children <13 years of age have not been established [see Patient Counseling Information (17)].

Safety and efficacy of ZYPREXA and fluoxetine in combination in children and adolescents (10 to 17 years of age) have been established for the acute treatment of depressive episodes associated with bipolar I disorder.

Safety and effectiveness of ZYPREXA and fluoxetine in combination in children <10 years of age have not been established.

8.5 Geriatric Use

Of the 2500 patients in premarketing clinical studies with oral olanzapine, 11% (263) were 65 years of age or over. In patients with schizophrenia, there was no indication of any different tolerability of olanzapine in the elderly compared to younger patients. Studies in elderly patients with dementia-related psychosis have suggested that there may be a different tolerability profile in this population compared to younger patients with schizophrenia. Elderly patients with dementia-related psychosis treated with olanzapine are at an increased risk of death compared to placebo. In placebo-controlled studies of olanzapine in elderly patients with dementia-related psychosis, there was a higher incidence of cerebrovascular adverse events (e.g., stroke, transient ischemic attack) in patients treated with olanzapine compared to patients treated with placebo. In 5 placebo-controlled studies of olanzapine in elderly patients with dementia-related psychosis (n=1184), the following adverse reactions were reported in olanzapine-treated patients at an incidence of at least 2% and significantly greater than placebo-treated patients: falls, somnolence, peripheral edema, abnormal gait, urinary incontinence, lethargy, increased weight, asthenia, pyrexia, pneumonia, dry mouth and visual hallucinations. The rate of discontinuation due to adverse reactions was greater with olanzapine than placebo (13% vs 7%). Elderly patients with dementia-related psychosis treated with olanzapine are at an increased risk of death compared to placebo. Olanzapine is not approved for the treatment of patients with dementia-related psychosis [see Boxed Warning, Warnings and Precautions (5.1), and Patient Counseling Information (17)]. Olanzapine is not approved for the treatment of patients with dementia-related psychosis. Also, the presence of factors that might decrease pharmacokinetic clearance or increase the pharmacodynamic response to olanzapine should lead to consideration of a lower starting dose for any geriatric patient [see Boxed Warning, Dosage and Administration (2.1), and Warnings and Precautions (5.1)].

Clinical studies of ZYPREXA and fluoxetine in combination did not include sufficient numbers of patients ≥65 years of age to determine whether they respond differently from younger patients.

9 DRUG ABUSE AND DEPENDENCE

9.3 Dependence

In studies prospectively designed to assess abuse and dependence potential, olanzapine was shown to have acute depressive CNS effects but little or no potential of abuse or physical dependence in rats administered oral doses up to 15 times the daily oral MRHD (20 mg) and rhesus monkeys administered oral doses up to 8 times the daily oral MRHD based on mg/m^2 body surface area.

Olanzapine has not been systematically studied in humans for its potential for abuse, tolerance, or physical dependence. While the clinical trials did not reveal any tendency for any drug-seeking behavior, these observations were not systematic, and it is not possible to predict on the basis of this limited experience the extent to which a CNS-active drug will be misused, diverted, and/or abused once marketed. Consequently, patients should be evaluated carefully for a history of drug abuse, and such patients should be observed closely for signs of misuse or abuse of olanzapine (e.g., development of tolerance, increases in dose, drug-seeking behavior).

10 OVERDOSAGE

10.1 Human Experience

In premarketing trials involving more than 3100 patients and/or normal subjects, accidental or intentional acute overdosage of olanzapine was identified in 67 patients. In the patient taking the largest identified amount, 300 mg, the only symptoms reported were drowsiness and slurred speech. In the limited number of patients who were evaluated in hospitals, including the patient taking 300 mg, there were no observations indicating an adverse change in laboratory analytes or ECG. Vital signs were usually within normal limits following overdoses.

In postmarketing reports of overdose with olanzapine alone, symptoms have been reported in the majority of cases. In symptomatic patients, symptoms with ≥10% incidence included agitation/aggressiveness, dysarthria, tachycardia, various extrapyramidal symptoms, and reduced level of consciousness ranging from sedation to coma. Among less commonly reported symptoms were the following potentially medically serious reactions: aspiration, cardiopulmonary arrest, cardiac arrhythmias (such as supraventricular tachycardia and 1 patient experiencing sinus pause with spontaneous resumption of normal rhythm), delirium, possible neuroleptic malignant syndrome, respiratory depression/arrest, convulsion, hypertension, and hypotension. Eli Lilly and Company has received reports of fatality in association with overdose of olanzapine alone. In 1 case of death, the amount of acutely ingested olanzapine was reported to be possibly as low as 450 mg of oral olanzapine; however, in another case, a patient was reported to survive an acute olanzapine ingestion of approximately 2 g of oral olanzapine.

10.2 Management of Overdose

There is no specific antidote to an overdose of ZYPREXA. The possibility of multiple drug involvement should be considered. Establish and maintain an airway and ensure adequate oxygenation and ventilation. Cardiovascular monitoring should commence immediately and should include continuous electrocardiographic monitoring to detect possible arrhythmias.

Contact a Certified Poison Control Center for the most up to date information on the management of overdosage (1-800-222-1222).

For specific information about overdosage with lithium or valproate, refer to the Overdosage section of the prescribing information for those products. For specific information about overdosage with olanzapine and fluoxetine in combination, refer to the Overdosage section of the Symbyax prescribing information.

11 DESCRIPTION

ZYPREXA (olanzapine) is an atypical antipsychotic that belongs to the thienobenzodiazepine class. The chemical designation is 2-methyl-4-(4-methyl-1-piperazinyl)-10H-thieno[2,3-b] [1,5]benzodiazepine. The molecular formula is C17H20N4S, which corresponds to a molecular weight of 312.44. The chemical structure is:

Olanzapine is a yellow crystalline solid, which is practically insoluble in water.

ZYPREXA tablets are intended for oral administration only.

Each tablet contains olanzapine equivalent to 2.5 mg (8 μmol), 5 mg (16 μmol), 7.5 mg (24 μmol), 10 mg (32 μmol), 15 mg (48 μmol), or 20 mg (64 μmol). Inactive ingredients are carnauba wax, crospovidone, hydroxypropyl cellulose, hypromellose, lactose, magnesium stearate, microcrystalline cellulose, and other inactive ingredients. The color coating contains Titanium Dioxide (all strengths), FD&C Blue No. 2 Aluminum Lake (15 mg), or Synthetic Red Iron Oxide (20 mg). The 2.5, 5, 7.5, and 10 mg tablets are imprinted with edible ink which contains FD&C Blue No. 2 Aluminum Lake.

ZYPREXA ZYDIS (olanzapine orally disintegrating tablets) is intended for oral administration only.

Each orally disintegrating tablet contains olanzapine equivalent to 5 mg (16 μmol), 10 mg (32 μmol), 15 mg (48 μmol) or 20 mg (64 μmol). It begins disintegrating in the mouth within seconds, allowing its contents to be subsequently swallowed with or without liquid. ZYPREXA ZYDIS (olanzapine orally disintegrating tablets) also contains the following inactive ingredients: gelatin, mannitol, aspartame, sodium methyl paraben, and sodium propyl paraben.

ZYPREXA IntraMuscular (olanzapine for injection) is intended for intramuscular use only.

Each single-dose vial provides for the administration of 10 mg (32 μmol) olanzapine with inactive ingredients 50 mg lactose monohydrate and 3.5 mg tartaric acid. Hydrochloric acid and/or sodium hydroxide may have been added during manufacturing to adjust pH.

12 CLINICAL PHARMACOLOGY

12.1 Mechanism of Action

The mechanism of action of olanzapine, in the listed indications is unclear. However, the efficacy of olanzapine in schizophrenia could be mediated through a combination of dopamine and serotonin type 2 (5HT2) antagonism.

12.2 Pharmacodynamics

Olanzapine binds with high affinity to the following receptors: serotonin 5HT2A/2C, 5HT6 (Ki=4, 11, and 5 nM, respectively), dopamine D1-4 (Ki=11-31 nM), histamine H1 (Ki=7 nM), and adrenergic α1 receptors (Ki=19 nM). Olanzapine is an antagonist with moderate affinity binding for serotonin 5HT3 (Ki=57 nM) and muscarinic M1-5 (Ki=73, 96, 132, 32, and 48 nM, respectively). Olanzapine binds with low affinity to GABAA, BZD, and β-adrenergic receptors (Ki>10 μM).

12.3 Pharmacokinetics

Oral Administration, Monotherapy — Olanzapine is well absorbed and reaches peak concentrations in approximately 6 hours following an oral dose. It is eliminated extensively by first pass metabolism, with approximately 40% of the dose metabolized before reaching the systemic circulation. Food does not affect the rate or extent of olanzapine absorption. Pharmacokinetic studies showed that ZYPREXA tablets and ZYPREXA ZYDIS (olanzapine orally disintegrating tablets) dosage forms of olanzapine are bioequivalent.

Olanzapine displays linear kinetics over the clinical dosing range. Its half-life ranges from 21 to 54 hours (5th to 95th percentile; mean of 30 hr), and apparent plasma clearance ranges from 12 to 47 L/hr (5th to 95th percentile; mean of 25 L/hr).

Administration of olanzapine once daily leads to steady-state concentrations in about 1 week that are approximately twice the concentrations after single doses. Plasma concentrations, half-life, and clearance of olanzapine may vary between individuals on the basis of smoking status, gender, and age.

Olanzapine is extensively distributed throughout the body, with a volume of distribution of approximately 1000 L. It is 93% bound to plasma proteins over the concentration range of 7 to 1100 ng/mL, binding primarily to albumin and α1-acid glycoprotein.

Metabolism and Elimination — Following a single oral dose of ^14C labeled olanzapine, 7% of the dose of olanzapine was recovered in the urine as unchanged drug, indicating that olanzapine is highly metabolized. Approximately 57% and 30% of the dose was recovered in the urine and feces, respectively. In the plasma, olanzapine accounted for only 12% of the AUC for total radioactivity, indicating significant exposure to metabolites. After multiple dosing, the major circulating metabolites were the 10-N-glucuronide, present at steady state at 44% of the concentration of olanzapine, and 4′-N-desmethyl olanzapine, present at steady state at 31% of the concentration of olanzapine. Both metabolites lack pharmacological activity at the concentrations observed.

Direct glucuronidation and cytochrome P450 (CYP) mediated oxidation are the primary metabolic pathways for olanzapine. In vitro studies suggest that CYPs 1A2 and 2D6, and the flavin-containing monooxygenase system are involved in olanzapine oxidation. CYP2D6 mediated oxidation appears to be a minor metabolic pathway in vivo, because the clearance of olanzapine is not reduced in subjects who are deficient in this enzyme.

Intramuscular Administration — ZYPREXA IntraMuscular results in rapid absorption with peak plasma concentrations occurring within 15 to 45 minutes. Based upon a pharmacokinetic study in healthy volunteers, a 5 mg dose of intramuscular olanzapine for injection produces, on average, a maximum plasma concentration approximately 5 times higher than the maximum plasma concentration produced by a 5 mg dose of oral olanzapine. Area under the curve achieved after an intramuscular dose is similar to that achieved after oral administration of the same dose. The half-life observed after intramuscular administration is similar to that observed after oral dosing. The pharmacokinetics are linear over the clinical dosing range. Metabolic profiles after intramuscular administration are qualitatively similar to metabolic profiles after oral administration.

Specific Populations

Renal Impairment — Because olanzapine is highly metabolized before excretion and only 7% of the drug is excreted unchanged, renal dysfunction alone is unlikely to have a major impact on the pharmacokinetics of olanzapine. The pharmacokinetic characteristics of olanzapine were similar in patients with severe renal impairment and normal subjects, indicating that dosage adjustment based upon the degree of renal impairment is not required. In addition, olanzapine is not removed by dialysis. The effect of renal impairment on metabolite elimination has not been studied.

Hepatic Impairment — Although the presence of hepatic impairment may be expected to reduce the clearance of olanzapine, a study of the effect of impaired liver function in subjects (n=6) with clinically significant (Childs Pugh Classification A and B) cirrhosis revealed little effect on the pharmacokinetics of olanzapine.

Geriatric — In a study involving 24 healthy subjects, the mean elimination half-life of olanzapine was about 1.5 times greater in elderly (≥65 years) than in nonelderly subjects (<65 years). Caution should be used in dosing the elderly, especially if there are other factors that might additively influence drug metabolism and/or pharmacodynamic sensitivity [see Dosage and Administration (2)].

Gender — Clearance of olanzapine is approximately 30% lower in women than in men. There were, however, no apparent differences between men and women in effectiveness or adverse effects. Dosage modifications based on gender should not be needed.

Smoking Status — Olanzapine clearance is about 40% higher in smokers than in nonsmokers, although dosage modifications are not routinely recommended.

Race — In vivo studies have shown that exposures are similar among Japanese, Chinese and Caucasians, especially after normalization for body weight differences. Dosage modifications for race are, therefore, not recommended.

Combined Effects — The combined effects of age, smoking, and gender could lead to substantial pharmacokinetic differences in populations. The clearance in young smoking males, for example, may be 3 times higher than that in elderly nonsmoking females. Dosing modification may be necessary in patients who exhibit a combination of factors that may result in slower metabolism of olanzapine [see Dosage and Administration (2)].

Adolescents (ages 13 to 17 years) — In clinical studies, most adolescents were nonsmokers and this population had a lower average body weight, which resulted in higher average olanzapine exposure compared to adults.

13 NONCLINICAL TOXICOLOGY

13.1 Carcinogenesis, Mutagenesis, Impairment of Fertility

Carcinogenesis — Oral carcinogenicity studies were conducted in mice and rats. Olanzapine was administered to mice in two 78-week studies at doses of 3, 10, 30/20 mg/kg/day (equivalent to 0.8-5 times the daily oral MRHD based on mg/m^2 body surface area) and 0.25, 2, 8 mg/kg/day (equivalent to 0.06-2 times the daily oral MRHD based on mg/m^2 body surface area). Rats were dosed for 2 years at doses of 0.25, 1, 2.5, 4 mg/kg/day (males) and 0.25, 1, 4, 8 mg/kg/day (females) (equivalent to 0.13-2 and 0.13-4 times the daily oral MRHD based on mg/m^2 body surface area, respectively). The incidence of liver hemangiomas and hemangiosarcomas was significantly increased in 1 mouse study in female mice at 2 times the daily oral MRHD based on mg/m^2 body surface area. These tumors were not increased in another mouse study in females dosed up to 2-5 times the daily oral MRHD based on mg/m^2 body surface area; in this study, there was a high incidence of early mortalities in males of the 30/20 mg/kg/day group. The incidence of mammary gland adenomas and adenocarcinomas was significantly increased in female mice dosed at ≥2 mg/kg/day and in female rats dosed at ≥4 mg/kg/day (0.5 and 2 times the daily oral MRHD based on mg/m^2 body surface area, respectively). Antipsychotic drugs have been shown to chronically elevate prolactin levels in rodents. Serum prolactin levels were not measured during the olanzapine carcinogenicity studies; however, measurements during subchronic toxicity studies showed that olanzapine elevated serum prolactin levels up to 4-fold in rats at the same doses used in the carcinogenicity study. An increase in mammary gland neoplasms has been found in rodents after chronic administration of other antipsychotic drugs and is considered to be prolactin mediated. The relevance for human risk of the finding of prolactin mediated endocrine tumors in rodents is unknown [see Warnings and Precautions (5.15)].

Mutagenesis — No evidence of genotoxic potential for olanzapine was found in the Ames reverse mutation test, in vivo micronucleus test in mice, the chromosomal aberration test in Chinese hamster ovary cells, unscheduled DNA synthesis test in rat hepatocytes, induction of forward mutation test in mouse lymphoma cells, or in vivo sister chromatid exchange test in bone marrow of Chinese hamsters.

Impairment of Fertility — In an oral fertility and reproductive performance study in rats, male mating performance, but not fertility, was impaired at a dose of 22.4 mg/kg/day and female fertility was decreased at a dose of 3 mg/kg/day (11 and 1.5 times the daily oral MRHD based on mg/m^2 body surface area, respectively). Discontinuance of olanzapine treatment reversed the effects on male mating performance. In female rats, the precoital period was increased and the mating index reduced at 5 mg/kg/day (2.5 times the daily oral MRHD based on mg/m^2 body surface area). Diestrous was prolonged and estrous delayed at 1.1 mg/kg/day (0.6 times the daily oral MRHD based on mg/m^2 body surface area); therefore olanzapine may produce a delay in ovulation.

13.2 Animal Toxicology and/or Pharmacology

In animal studies with olanzapine, the principal hematologic findings were reversible peripheral cytopenias in individual dogs dosed at 10 mg/kg (17 times the daily oral MRHD based on mg/m^2 body surface area), dose-related decreases in lymphocytes and neutrophils in mice, and lymphopenia in rats. A few dogs treated with 10 mg/kg developed reversible neutropenia and/or reversible hemolytic anemia between 1 and 10 months of treatment. Dose-related decreases in lymphocytes and neutrophils were seen in mice given doses of 10 mg/kg (equal to 2 times the daily oral MRHD based on mg/m^2 body surface area) in studies of 3 months' duration. Nonspecific lymphopenia, consistent with decreased body weight gain, occurred in rats receiving 22.5 mg/kg (11 times the daily oral MRHD based on mg/m^2 body surface area) for 3 months or 16 mg/kg (8 times the daily oral MRHD based on mg/m^2 body surface area) for 6 or 12 months. No evidence of bone marrow cytotoxicity was found in any of the species examined. Bone marrows were normocellular or hypercellular, indicating that the reductions in circulating blood cells were probably due to peripheral (non-marrow) factors.

14 CLINICAL STUDIES

When using ZYPREXA and fluoxetine in combination, also refer to the Clinical Studies section of the package insert for Symbyax.

14.1 Schizophrenia

Adults

The efficacy of oral olanzapine in the treatment of schizophrenia was established in 2 short-term (6-week) controlled trials of adult inpatients who met DSM III-R criteria for schizophrenia. A single haloperidol arm was included as a comparative treatment in 1 of the 2 trials, but this trial did not compare these 2 drugs on the full range of clinically relevant doses for both.

Several instruments were used for assessing psychiatric signs and symptoms in these studies, among them the Brief Psychiatric Rating Scale (BPRS), a multi-item inventory of general psychopathology traditionally used to evaluate the effects of drug treatment in schizophrenia. The BPRS psychosis cluster (conceptual disorganization, hallucinatory behavior, suspiciousness, and unusual thought content) is considered a particularly useful subset for assessing actively psychotic schizophrenic patients. A second traditional assessment, the Clinical Global Impression (CGI), reflects the impression of a skilled observer, fully familiar with the manifestations of schizophrenia, about the overall clinical state of the patient. In addition, 2 more recently developed scales were employed; these included the 30-item Positive and Negative Symptoms Scale (PANSS), in which are embedded the 18 items of the BPRS, and the Scale for Assessing Negative Symptoms (SANS). The trial summaries below focus on the following outcomes: PANSS total and/or BPRS total; BPRS psychosis cluster; PANSS negative subscale or SANS; and CGI Severity. The results of the trials follow:

(1) In a 6-week, placebo-controlled trial (n=149) involving 2 fixed olanzapine doses of 1 and 10 mg/day (once daily schedule), olanzapine, at 10 mg/day (but not at 1 mg/day), was superior to placebo on the PANSS total score (also on the extracted BPRS total), on the BPRS psychosis cluster, on the PANSS Negative subscale, and on CGI Severity.

(2) In a 6-week, placebo-controlled trial (n=253) involving 3 fixed dose ranges of olanzapine (5 ± 2.5 mg/day, 10 ± 2.5 mg/day, and 15 ± 2.5 mg/day) on a once daily schedule, the 2 highest olanzapine dose groups (actual mean doses of 12 and 16 mg/day, respectively) were superior to placebo on BPRS total score, BPRS psychosis cluster, and CGI severity score; the highest olanzapine dose group was superior to placebo on the SANS. There was no clear advantage for the high-dose group over the medium-dose group.

(3) In a longer-term trial, adult outpatients (n=326) who predominantly met DSM-IV criteria for schizophrenia and who remained stable on olanzapine during open-label treatment for at least 8 weeks were randomized to continuation on their current olanzapine doses (ranging from 10 to 20 mg/day) or to placebo. The follow-up period to observe patients for relapse, defined in terms of increases in BPRS positive symptoms or hospitalization, was planned for 12 months, however, criteria were met for stopping the trial early due to an excess of placebo relapses compared to olanzapine relapses, and olanzapine was superior to placebo on time to relapse, the primary outcome for this study. Thus, olanzapine was more effective than placebo at maintaining efficacy in patients stabilized for approximately 8 weeks and followed for an observation period of up to 8 months.

Examination of population subsets (race and gender) did not reveal any differential responsiveness on the basis of these subgroupings.

Adolescents

The efficacy of oral olanzapine in the acute treatment of schizophrenia in adolescents (ages 13 to 17 years) was established in a 6-week double-blind, placebo-controlled, randomized trial of inpatients and outpatients with schizophrenia (n=107) who met diagnostic criteria according to DSM-IV-TR and confirmed by the Kiddie Schedule for Affective Disorders and Schizophrenia for School Aged Children-Present and Lifetime Version (K-SADS-PL).

The primary rating instrument used for assessing psychiatric signs and symptoms in this trial was the Anchored Version of the Brief Psychiatric Rating Scale for Children (BPRS-C) total score.

In this flexible-dose trial, olanzapine 2.5 to 20 mg/day (mean modal dose 12.5 mg/day, mean dose of 11.1 mg/day) was more effective than placebo in the treatment of adolescents diagnosed with schizophrenia, as supported by the statistically significantly greater mean reduction in BPRS-C total score for patients in the olanzapine treatment group than in the placebo group.

While there is no body of evidence available to answer the question of how long the adolescent patient treated with ZYPREXA should be maintained, maintenance efficacy can be extrapolated from adult data along with comparisons of olanzapine pharmacokinetic parameters in adult and adolescent patients. It is generally recommended that responding patients be continued beyond the acute response, but at the lowest dose needed to maintain remission. Patients should be periodically reassessed to determine the need for maintenance treatment.

14.2 Bipolar I Disorder (Manic or Mixed Episodes)

Adults

Monotherapy — The efficacy of oral olanzapine in the treatment of manic or mixed episodes was established in 2 short-term (one 3-week and one 4-week) placebo-controlled trials in adult patients who met the DSM-IV criteria for bipolar I disorder with manic or mixed episodes. These trials included patients with or without psychotic features and with or without a rapid-cycling course.

The primary rating instrument used for assessing manic symptoms in these trials was the Young Mania Rating Scale (Y-MRS), an 11-item clinician-rated scale traditionally used to assess the degree of manic symptomatology (irritability, disruptive/aggressive behavior, sleep, elevated mood, speech, increased activity, sexual interest, language/thought disorder, thought content, appearance, and insight) in a range from 0 (no manic features) to 60 (maximum score). The primary outcome in these trials was change from baseline in the Y-MRS total score. The results of the trials follow:

(1) In one 3-week placebo-controlled trial (n=67) which involved a dose range of olanzapine (5-20 mg/day, once daily, starting at 10 mg/day), olanzapine was superior to placebo in the reduction of Y-MRS total score. In an identically designed trial conducted simultaneously with the first trial, olanzapine demonstrated a similar treatment difference, but possibly due to sample size and site variability, was not shown to be superior to placebo on this outcome.

(2) In a 4-week placebo-controlled trial (n=115) which involved a dose range of olanzapine (5-20 mg/day, once daily, starting at 15 mg/day), olanzapine was superior to placebo in the reduction of Y-MRS total score.

(3) In another trial, 361 patients meeting DSM-IV criteria for a manic or mixed episode of bipolar I disorder who had responded during an initial open-label treatment phase for about 2 weeks, on average, to olanzapine 5 to 20 mg/day were randomized to either continuation of olanzapine at their same dose (n=225) or to placebo (n=136), for observation of relapse. Approximately 50% of the patients had discontinued from the olanzapine group by day 59 and 50% of the placebo group had discontinued by day 23 of double-blind treatment. Response during the open-label phase was defined by having a decrease of the Y-MRS total score to ≤12 and HAM-D 21 to ≤8. Relapse during the double-blind phase was defined as an increase of the Y-MRS or HAM-D 21 total score to ≥15, or being hospitalized for either mania or depression. In the randomized phase, patients receiving continued olanzapine experienced a significantly longer time to relapse.

Adjunct to Lithium or Valproate — The efficacy of oral olanzapine with concomitant lithium or valproate in the treatment of manic or mixed episodes was established in 2 controlled trials in patients who met the DSM-IV criteria for bipolar I disorder with manic or mixed episodes. These trials included patients with or without psychotic features and with or without a rapid-cycling course. The results of the trials follow:

(1) In one 6-week placebo-controlled combination trial, 175 outpatients on lithium or valproate therapy with inadequately controlled manic or mixed symptoms (Y-MRS ≥16) were randomized to receive either olanzapine or placebo, in combination with their original therapy. Olanzapine (in a dose range of 5-20 mg/day, once daily, starting at 10 mg/day) combined with lithium or valproate (in a therapeutic range of 0.6 mEq/L to 1.2 mEq/L or 50 μg/mL to 125 μg/mL, respectively) was superior to lithium or valproate alone in the reduction of Y-MRS total score.

(2) In a second 6-week placebo-controlled combination trial, 169 outpatients on lithium or valproate therapy with inadequately controlled manic or mixed symptoms (Y-MRS ≥16) were randomized to receive either olanzapine or placebo, in combination with their original therapy. Olanzapine (in a dose range of 5-20 mg/day, once daily, starting at 10 mg/day) combined with lithium or valproate (in a therapeutic range of 0.6 mEq/L to 1.2 mEq/L or 50 μg/mL to 125 μg/mL, respectively) was superior to lithium or valproate alone in the reduction of Y-MRS total score.

Adolescents

Acute Monotherapy — The efficacy of oral olanzapine in the treatment of acute manic or mixed episodes in adolescents (ages 13 to 17 years) was established in a 3-week, double-blind, placebo-controlled, randomized trial of adolescent inpatients and outpatients who met the diagnostic criteria for manic or mixed episodes associated with bipolar I disorder (with or without psychotic features) according to the DSM-IV-TR (n=161). Diagnosis was confirmed by the K-SADS-PL.

The primary rating instrument used for assessing manic symptoms in this trial was the Adolescent Structured Young-Mania Rating Scale (Y-MRS) total score.

In this flexible-dose trial, olanzapine 2.5 to 20 mg/day (mean modal dose 10.7 mg/day, mean dose of 8.9 mg/day) was more effective than placebo in the treatment of adolescents with manic or mixed episodes associated with bipolar I disorder, as supported by the statistically significantly greater mean reduction in Y-MRS total score for patients in the olanzapine treatment group than in the placebo group.

While there is no body of evidence available to answer the question of how long the adolescent patient treated with ZYPREXA should be maintained, maintenance efficacy can be extrapolated from adult data along with comparisons of olanzapine pharmacokinetic parameters in adult and adolescent patients. It is generally recommended that responding patients be continued beyond the acute response, but at the lowest dose needed to maintain remission. Patients should be periodically reassessed to determine the need for maintenance treatment.

14.3 Agitation Associated with Schizophrenia and Bipolar I Mania

The efficacy of intramuscular olanzapine for injection for the treatment of agitation was established in 3 short-term (24 hours of IM treatment) placebo-controlled trials in agitated adult inpatients from 2 diagnostic groups: schizophrenia and bipolar I disorder (manic or mixed episodes). Each of the trials included a single active comparator treatment arm of either haloperidol injection (schizophrenia studies) or lorazepam injection (bipolar I mania study). Patients enrolled in the trials needed to be: (1) judged by the clinical investigators as clinically agitated and clinically appropriate candidates for treatment with intramuscular medication, and (2) exhibiting a level of agitation that met or exceeded a threshold score of ≥14 on the 5 items comprising the Positive and Negative Syndrome Scale (PANSS) Excited Component (i.e., poor impulse control, tension, hostility, uncooperativeness and excitement items) with at least 1 individual item score ≥4 using a 1-7 scoring system (1=absent, 4=moderate, 7=extreme). In the studies, the mean baseline PANSS Excited Component score was 18.4, with scores ranging from 13 to 32 (out of a maximum score of 35), thus suggesting predominantly moderate levels of agitation with some patients experiencing mild or severe levels of agitation. The primary efficacy measure used for assessing agitation signs and symptoms in these trials was the change from baseline in the PANSS Excited Component at 2 hours post-injection. Patients could receive up to 3 injections during the 24 hour IM treatment periods; however, patients could not receive the second injection until after the initial 2 hour period when the primary efficacy measure was assessed. The results of the trials follow:

(1) In a placebo-controlled trial in agitated inpatients meeting DSM-IV criteria for schizophrenia (n=270), 4 fixed intramuscular olanzapine for injection doses of 2.5 mg, 5 mg, 7.5 mg and 10 mg were evaluated. All doses were statistically superior to placebo on the PANSS Excited Component at 2 hours post-injection. However, the effect was larger and more consistent for the 3 highest doses. There were no significant pairwise differences for the 7.5 and 10 mg doses over the 5 mg dose.

(2) In a second placebo-controlled trial in agitated inpatients meeting DSM-IV criteria for schizophrenia (n=311), 1 fixed intramuscular olanzapine for injection dose of 10 mg was evaluated. Olanzapine for injection was statistically superior to placebo on the PANSS Excited Component at 2 hours post-injection.

(3) In a placebo-controlled trial in agitated inpatients meeting DSM-IV criteria for bipolar I disorder (and currently displaying an acute manic or mixed episode with or without psychotic features) (n=201), 1 fixed intramuscular olanzapine for injection dose of 10 mg was evaluated. Olanzapine for injection was statistically superior to placebo on the PANSS Excited Component at 2 hours post-injection.

Examination of population subsets (age, race, and gender) did not reveal any differential responsiveness on the basis of these subgroupings.

16 HOW SUPPLIED/STORAGE AND HANDLING

16.1 How Supplied

The ZYPREXA 2.5 mg, 5 mg, 7.5 mg, and 10 mg tablets are white, round, and imprinted in blue ink with LILLY and tablet number. The 15 mg tablets are elliptical, blue, and debossed with LILLY and tablet number. The 20 mg tablets are elliptical, pink, and debossed with LILLY and tablet number. The tablets are available as follows:

 | TABLET STRENGTH
 | 2.5 mg | 5 mg | 7.5 mg | 10 mg | 15 mg | 20 mg
Tablet No. | 4112 | 4115 | 4116 | 4117 | 4415 | 4420
Identification | LILLY | LILLY | LILLY | LILLY | LILLY | LILLY
 | 4112 | 4115 | 4116 | 4117 | 4415 | 4420
NDC Codes:
Bottles 30 | NDC 61269-630-30 | NDC 61269-631-30 | NDC 61269-632-30 | NDC 61269-633-30 | NDC 61269-634-30 | NDC 61269-635-30

ZYPREXA ZYDIS (olanzapine orally disintegrating tablets) are yellow, round, and debossed with the tablet strength. The tablets are available as follows:

 | TABLET STRENGTH
ZYPREXA ZYDIS Tablets | 5 mg | 10 mg | 15 mg | 20 mg
Tablet No. | 4453 | 4454 | 4455 | 4456
Debossed | 5 | 10 | 15 | 20
NDC Codes:
Dose Pack 30 (Child Resistant) | NDC 61269-650-35 | NDC 61269-651-35 | NDC 61269-652-35 | NDC 61269-653-35
ZYPREXA is a registered trademark of CHEPLAPHARM.
ZYDIS is a registered trademark of Catalent Pharma Solutions.

ZYPREXA IntraMuscular is available in: NDC 61269-640-20 – 10 mg single-dose vial (1s)

16.2 Storage and Handling

Store ZYPREXA tablets, ZYPREXA ZYDIS, and ZYPREXA IntraMuscular vials (before reconstitution) at controlled room temperature, 20° to 25°C (68° to 77°F) [see USP]. Reconstituted ZYPREXA IntraMuscular may be stored at controlled room temperature, 20° to 25°C (68° to 77°F) [see USP] for up to 1 hour if necessary. Discard any unused portion of reconstituted ZYPREXA IntraMuscular. The USP defines controlled room temperature as a temperature maintained thermostatically that encompasses the usual and customary working environment of 20° to 25°C (68° to 77°F); that results in a mean kinetic temperature calculated to be not more than 25°C; and that allows for excursions between 15° and 30°C (59° and 86°F) that are experienced in pharmacies, hospitals, and warehouses.

Protect ZYPREXA tablets and ZYPREXA ZYDIS from light and moisture. Protect ZYPREXA IntraMuscular from light, do not freeze.

17 PATIENT COUNSELING INFORMATION

Advise the patient to read the FDA-approved patient labeling (Medication Guide) for the oral formulations.

Patients should be advised of the following issues and asked to alert their prescriber if these occur while taking ZYPREXA as monotherapy or in combination with fluoxetine. If you do not think you are getting better or have any concerns about your condition while taking ZYPREXA, call your doctor. When using ZYPREXA and fluoxetine in combination, also refer to the Patient Counseling Information section of the package insert for Symbyax.

Elderly Patients with Dementia-Related Psychosis: Increased Mortality and Cerebrovascular Adverse Events (CVAE), Including Stroke

Patients and caregivers should be advised that elderly patients with dementia-related psychosis treated with antipsychotic drugs are at an increased risk of death. Patients and caregivers should be advised that elderly patients with dementia-related psychosis treated with ZYPREXA had a significantly higher incidence of cerebrovascular adverse events (e.g., stroke, transient ischemic attack) compared with placebo.

ZYPREXA is not approved for elderly patients with dementia-related psychosis [see Boxed Warning and Warnings and Precautions (5.1)].

Neuroleptic Malignant Syndrome (NMS)

Patients and caregivers should be counseled that a potentially fatal symptom complex sometimes referred to as NMS has been reported in association with administration of antipsychotic drugs, including ZYPREXA. Signs and symptoms of NMS include hyperpyrexia, muscle rigidity, altered mental status, and evidence of autonomic instability (irregular pulse or blood pressure, tachycardia, diaphoresis, and cardiac dysrhythmia) [see Warnings and Precautions (5.3)].

Drug Reaction with Eosinophilia and Systemic Symptoms (DRESS)

Patients should be advised to report to their health care provider at the earliest onset of any signs and symptoms that may be associated with drug reaction with eosinophilia and systemic symptoms (DRESS) [see Warnings and Precautions (5.4)].

Hyperglycemia and Diabetes Mellitus

Patients should be advised of the potential risk of hyperglycemia-related adverse reactions. Patients should be monitored regularly for worsening of glucose control. Patients who have diabetes should follow their doctor's instructions about how often to check their blood sugar while taking ZYPREXA [see Warnings and Precautions (5.5)].

Dyslipidemia

Patients should be counseled that dyslipidemia has occurred during treatment with ZYPREXA. Patients should have their lipid profile monitored regularly [see Warnings and Precautions (5.5)].

Weight Gain

Patients should be counseled that weight gain has occurred during treatment with ZYPREXA. Patients should have their weight monitored regularly [see Warnings and Precautions (5.5)].

Orthostatic Hypotension

Patients should be advised of the risk of orthostatic hypotension, especially during the period of initial dose titration and in association with the use of concomitant drugs that may potentiate the orthostatic effect of ZYPREXA, e.g., diazepam or alcohol [see Warnings and Precautions (5.7) and Drug Interactions (7)]. Patients should be advised to change positions carefully to help prevent orthostatic hypotension, and to lie down if they feel dizzy or faint, until they feel better. Patients should be advised to call their doctor if they experience any of the following signs and symptoms associated with orthostatic hypotension: dizziness, fast or slow heartbeat, or fainting.

Potential for Cognitive and Motor Impairment

Because ZYPREXA has the potential to impair judgment, thinking, or motor skills, patients should be cautioned about operating hazardous machinery, including automobiles, until they are reasonably certain that ZYPREXA therapy does not affect them adversely [see Warnings and Precautions (5.12)].

Body Temperature Regulation

Patients should be advised regarding appropriate care in avoiding overheating and dehydration. Patients should be advised to call their doctor right away if they become severely ill and have some or all of these symptoms of dehydration: sweating too much or not at all, dry mouth, feeling very hot, feeling thirsty, not able to produce urine [see Warnings and Precautions (5.13)].

Concomitant Medication

Patients should be advised to inform their healthcare providers if they are taking, or plan to take, Symbyax. Patients should also be advised to inform their healthcare providers if they are taking, plan to take, or have stopped taking any prescription or over-the-counter drugs, including herbal supplements, since there is a potential for interactions [see Drug Interactions (7)].

Alcohol

Patients should be advised to avoid alcohol while taking ZYPREXA [see Drug Interactions (7)].

Phenylketonurics

ZYPREXA ZYDIS (olanzapine orally disintegrating tablets) contains phenylalanine (0.34, 0.45, 0.67, or 0.90 mg per 5, 10, 15, or 20 mg tablet, respectively) [see Description (11)].

Use in Specific Populations

Pregnancy — Advise women to notify their healthcare provider if they become pregnant or intend to become pregnant during treatment with ZYPREXA. Advise patients that ZYPREXA may cause extrapyramidal and/or withdrawal symptoms (agitation, hypertonia, hypotonia, tremor, somnolence, respiratory distress, and feeding disorder) in a neonate. Advise patients that there is a pregnancy exposure registry that monitors pregnancy outcomes in women exposed to ZYPREXA during pregnancy [see Use in Specific Populations (8.1)].

Lactation — Advise breastfeeding women using ZYPREXA to monitor infants for excess sedation, irritability, poor feeding and extrapyramidal symptoms (tremors and abnormal muscle movements) and to seek medical care if they notice these signs [see Use in Specific Populations (8.3)].

Infertility — Advise females of reproductive potential that ZYPREXA may impair fertility due to an increase in serum prolactin levels. The effects on fertility are reversible [see Use in Specific Populations (8.3)].

Pediatric Use — ZYPREXA is indicated for treatment of schizophrenia and manic or mixed episodes associated with bipolar I disorder in adolescents 13 to 17 years of age. Compared to patients from adult clinical trials, adolescents were likely to gain more weight, experience increased sedation, and have greater increases in total cholesterol, triglycerides, LDL cholesterol, prolactin, and hepatic aminotransferase levels. Patients should be counseled about the potential long-term risks associated with ZYPREXA and advised that these risks may lead them to consider other drugs first [see Indications and Usage (1.1, 1.2)]. Safety and effectiveness of ZYPREXA in patients under 13 years of age have not been established. Safety and efficacy of ZYPREXA and fluoxetine in combination in patients 10 to 17 years of age have been established for the acute treatment of depressive episodes associated with bipolar I disorder. Safety and effectiveness of ZYPREXA and fluoxetine in combination in patients <10 years of age have not been established [see Warnings and Precautions (5.5) and Use in Specific Populations (8.4)].

Need for Comprehensive Treatment Program in Pediatric Patients

ZYPREXA is indicated as an integral part of a total treatment program for pediatric patients with schizophrenia and bipolar disorder that may include other measures (psychological, educational, social) for patients with the disorder. Effectiveness and safety of ZYPREXA have not been established in pediatric patients less than 13 years of age. Atypical antipsychotics are not intended for use in the pediatric patient who exhibits symptoms secondary to environmental factors and/or other primary psychiatric disorders. Appropriate educational placement is essential and psychosocial intervention is often helpful. The decision to prescribe atypical antipsychotic medication will depend upon the healthcare provider's assessment of the chronicity and severity of the patient's symptoms [see Indications and Usage (1.3)].

Distributed by: H2-Pharma, LLC

Montgomery, AL 36117, USA

Licensed by: CHEPLAPHARM Registration GmbH, Weiler Straße5e, 79540 Lörrach, Germany

CHEPLAPHARM Registration GmbH under the license of CHEPLAPHARM Schweiz GmbH

Medication Guide

ZYPREXA® (zy-PREX-a)

(olanzapine)

Tablet

ZYPREXA® ZYDIS® (zy-PREX-a ZY-dis)

(olanzapine)

Tablet, Orally Disintegrating

Read the Medication Guide that comes with ZYPREXA before you start taking it and each time you get a refill. There may be new information. This Medication Guide does not take the place of talking to your doctor about your medical condition or treatment. Talk with your doctor or pharmacist if there is something you do not understand or you want to learn more about ZYPREXA.

What is the most important information I should know about ZYPREXA?

ZYPREXA may cause serious side effects, including:

1. Increased risk of death in elderly people who are confused, have memory loss and have lost touch with reality (dementia-related psychosis).
2. High blood sugar (hyperglycemia).
3. High fat levels in your blood (increased cholesterol and triglycerides), especially in teenagers age 13 to 17 or when used in combination with fluoxetine in children age 10 to 17.
4. Weight gain, especially in teenagers age 13 to 17 or when used in combination with fluoxetine in children age 10 to 17.

These serious side effects are described below.

1. Increased risk of death in elderly people who are confused, have memory loss and have lost touch with reality (dementia-related psychosis). ZYPREXA is not approved for treating psychosis in elderly people with dementia.
2. High blood sugar (hyperglycemia).High blood sugar can happen if you have diabetes already or if you have never had diabetes. High blood sugar could lead to:
  - a build up of acid in your blood due to ketones (ketoacidosis)
  - coma
  - death
  Your doctor should do tests to check your blood sugar before you start taking ZYPREXA and during treatment. In people who do not have diabetes, sometimes high blood sugar goes away when ZYPREXA is stopped. People with diabetes and some people who did not have diabetes before taking ZYPREXA need to take medicine for high blood sugar even after they stop taking ZYPREXA.
  If you have diabetes, follow your doctor's instructions about how often to check your blood sugar while taking ZYPREXA.
  Call your doctorif you have any of these symptoms of high blood sugar (hyperglycemia) while taking ZYPREXA:
  - feel very thirsty
  - need to urinate more than usual
  - feel very hungry
  - feel weak or tired
  - feel sick to your stomach
  - feel confused or your breath smells fruity
3. High fat levels in your blood (cholesterol and triglycerides). High fat levels may happen in people treated with ZYPREXA, especially in teenagers (13 to 17 years old), or when used in combination with fluoxetine in children (10 to 17 years old). You may not have any symptoms, so your doctor should do blood tests to check your cholesterol and triglyceride levels before you start taking ZYPREXA and during treatment.
4. Weight gain. Weight gain is very common in people who take ZYPREXA. Teenagers (13 to 17 years old) are more likely to gain weight and to gain more weight than adults. Children (10 to 17 years old) are also more likely to gain weight and to gain more weight than adults when ZYPREXA is used in combination with fluoxetine. Some people may gain a lot of weight while taking ZYPREXA, so you and your doctor should check your weight regularly. Talk to your doctor about ways to control weight gain, such as eating a healthy, balanced diet, and exercising.

What is ZYPREXA?

ZYPREXA is a prescription medicine used to treat:

- schizophrenia in people age 13 or older.
- bipolar disorder, including:
  - manic or mixed episodes that happen with bipolar I disorder in people age 13 or older.
  - manic or mixed episodes that happen with bipolar I disorder, when used with the medicine lithium or valproate, in adults.
  - long-term treatment of bipolar I disorder in adults.
- episodes of depression that happen with bipolar I disorder, when used with the medicine fluoxetine (Prozac®) in people age 10 or older.
- episodes of depression that do not get better after 2 other medicines, also called treatment resistant depression, when used with the medicine fluoxetine (Prozac), in adults.

ZYPREXA has not been approved for use in children under 13 years of age. ZYPREXA in combination with fluoxetine has not been approved for use in children under 10 years of age.

The symptoms of schizophrenia include hearing voices, seeing things that are not there, having beliefs that are not true, and being suspicious or withdrawn.

The symptoms of bipolar I disorder include alternating periods of depression and high or irritable mood, increased activity and restlessness, racing thoughts, talking fast, impulsive behavior, and a decreased need for sleep.

The symptoms of treatment resistant depression include decreased mood, decreased interest, increased guilty feelings, decreased energy, decreased concentration, changes in appetite, and suicidal thoughts or behavior.

Some of your symptoms may improve with treatment. If you do not think you are getting better, call your doctor.

What should I tell my doctor before taking ZYPREXA?

ZYPREXA may not be right for you. Before starting ZYPREXA, tell your doctor if you have or had:

- heart problems
- seizures
- diabetes or high blood sugar levels (hyperglycemia)
- high cholesterol or triglyceride levels in your blood
- liver problems
- low or high blood pressure
- strokes or "mini-strokes" also called transient ischemic attacks (TIAs)
- Alzheimer's disease
- narrow-angle glaucoma
- enlarged prostate in men
- bowel obstruction
- phenylketonuria, because ZYPREXA ZYDIS contains phenylalanine
- breast cancer
- thoughts of suicide or hurting yourself
- any other medical condition
- are pregnant or plan to become pregnant. It is not known if ZYPREXA will harm your unborn baby.
  - If you become pregnant while receiving ZYPREXA, talk to your healthcare provider about registering with the National Pregnancy Registry for Atypical Antipsychotics. You can register by calling 1-866-961-2388 or go to http://womensmentalhealth.org/clinical-and-research-programs/pregnancyregistry/.
- are breast-feeding or plan to breast-feed. ZYPREXA passes into your breast milk. Talk to your doctor about the best way to feed your baby if you take ZYPREXA.

Tell your doctor if you exercise a lot or are in hot places often.

The symptoms of bipolar I disorder, treatment resistant depression, or schizophrenia may include thoughts of suicide or of hurting yourself or others. If you have these thoughts at any time, tell your doctor or go to an emergency room right away.

Tell your doctor about all the medicines that you take, including prescription and nonprescription medicines, vitamins, and herbal supplements. ZYPREXA and some medicines may interact with each other and may not work as well, or cause possible serious side effects. Your doctor can tell you if it is safe to take ZYPREXA with your other medicines. Do not start or stop any medicine while taking ZYPREXA without talking to your doctor first.

How should I take ZYPREXA?

- Take ZYPREXA exactly as prescribed. Your doctor may need to change (adjust) the dose of ZYPREXA until it is right for you.
- If you miss a dose of ZYPREXA, take the missed dose as soon as you remember. If it is almost time for the next dose, just skip the missed dose and take your next dose at the regular time. Do not take two doses of ZYPREXA at the same time.
- To prevent serious side effects, do not stop taking ZYPREXA suddenly. If you need to stop taking ZYPREXA, your doctor can tell you how to safely stop taking it.
- If you take too much ZYPREXA, call your doctor or poison control center at 1-800-222-1222 right away, or get emergency treatment.
- ZYPREXA can be taken with or without food.
- ZYPREXA is usually taken one time each day.
- Take ZYPREXA ZYDIS as follows:
  - Be sure that your hands are dry.
  - Open the sachet and peel back the foil on the blister. Do not push the tablet through the foil.
  - As soon as you open the blister, remove the tablet and put it into your mouth.
  - The tablet will disintegrate quickly in your saliva so that you can easily swallow it with or without drinking liquid.
- Call your doctor if you do not think you are getting better or have any concerns about your condition while taking ZYPREXA.

What should I avoid while taking ZYPREXA?

- ZYPREXA can cause sleepiness and may affect your ability to make decisions, think clearly, or react quickly. You should not drive, operate heavy machinery, or do other dangerous activities until you know how ZYPREXA affects you.
- Avoid drinking alcohol while taking ZYPREXA. Drinking alcohol while you take ZYPREXA may make you sleepier than if you take ZYPREXA alone.

What are the possible side effects of ZYPREXA?

Serious side effects may happen when you take ZYPREXA, including:

- See "What is the most important information I should know about ZYPREXA?", which describes the increased risk of death in elderly people with dementia-related psychosis and the risks of high blood sugar, high cholesterol and triglyceride levels, and weight gain.
- Increased incidence of stroke or "mini-strokes" called transient ischemic attacks (TIAs) in elderly people with dementia-related psychosis (elderly people who have lost touch with reality due to confusion and memory loss). ZYPREXA is not approved for these patients.
- Neuroleptic Malignant Syndrome (NMS):NMS is a rare but very serious condition that can happen in people who take antipsychotic medicines, including ZYPREXA. NMS can cause death and must be treated in a hospital. Call your doctor right away if you become severely ill and have any of these symptoms:
  - high fever
  - excessive sweating
  - rigid muscles
  - confusion
  - changes in your breathing, heartbeat, and blood pressure.
- Drug Reaction with Eosinophilia and Systemic Symptoms (DRESS): DRESS can occur with ZYPREXA. Features of DRESS may include rash, fever, swollen glands and other internal organ involvement such as liver, kidney, lung and heart. DRESS is sometimes fatal; therefore, tell your doctor immediately if you experience any of these signs.
- Tardive Dyskinesia: This condition causes body movements that keep happening and that you can not control. These movements usually affect the face and tongue. Tardive dyskinesia may not go away, even if you stop taking ZYPREXA. It may also start after you stop taking ZYPREXA. Tell your doctor if you get any body movements that you can not control.
- Decreased blood pressure when you change positions, with symptoms of dizziness, fast or slow heartbeat, or fainting.
- Difficulty swallowing, that can cause food or liquid to get into your lungs.
- Seizures: Tell your doctor if you have a seizure during treatment with ZYPREXA.
- Problems with control of body temperature:You could become very hot, for instance when you exercise a lot or stay in an area that is very hot. It is important for you to drink water to avoid dehydration. Call your doctor right away if you become severely ill and have any of these symptoms of dehydration:
  - sweating too much or not at all
  - dry mouth
  - feeling very hot
  - feeling thirsty
  - not able to produce urine.

Common side effects of ZYPREXA include: lack of energy, dry mouth, increased appetite, sleepiness, tremor (shakes), having hard or infrequent stools, dizziness, changes in behavior, or restlessness.

Other common side effects in teenagers (13-17 years old) include: headache, stomach-area (abdominal) pain, pain in your arms or legs, or tiredness. Teenagers experienced greater increases in prolactin, liver enzymes, and sleepiness, as compared with adults.

Tell your doctor about any side effect that bothers you or that does not go away.

These are not all the possible side effects with ZYPREXA. For more information, ask your doctor or pharmacist.

Call your doctor for medical advice about side effects. You may report side effects to FDA at 1-800-FDA-1088.

How should I store ZYPREXA?

- Store ZYPREXA at room temperature, between 68°F to 77°F (20°C to 25°C).
- Keep ZYPREXA away from light.
- Keep ZYPREXA dry and away from moisture.

Keep ZYPREXA and all medicines out of the reach of children.

General information about ZYPREXA

Medicines are sometimes prescribed for purposes other than those listed in a Medication Guide. Do not use ZYPREXA for a condition for which it was not prescribed. Do not give ZYPREXA to other people, even if they have the same condition. It may harm them.

This Medication Guide summarizes the most important information about ZYPREXA. If you would like more information, talk with your doctor. You can ask your doctor or pharmacist for information about ZYPREXA that was written for healthcare professionals. For more information about ZYPREXA call 1-866-770-9010.

What are the ingredients in ZYPREXA?

Active ingredient: olanzapine

Inactive ingredients:

Tablets — carnauba wax, crospovidone, hydroxypropyl cellulose, hypromellose, lactose, magnesium stearate, microcrystalline cellulose, and other inactive ingredients. The color coating contains: Titanium Dioxide, FD&C Blue No. 2 Aluminum Lake, or Synthetic Red Iron Oxide.

ZYDIS — gelatin, mannitol, aspartame, sodium methyl paraben, and sodium propyl paraben.

This Medication Guide has been approved by the U.S. Food and Drug Administration.

Medication Guide revised October, 2023

Distributed by: H2-Pharma, LLC
Montgomery, AL 36117, USA

Licensed by:
CHEPLAPHARM Registration GmbH
Weilerstr. 5e, 79540 Lörrach, Germany

CHEPLAPHARM Registration GmbH under the license of CHEPLAPHARM Schweiz GmbH

PRINCIPAL DISPLAY PANEL - 2.5 mg Tablet Bottle Label

NDC 61269-630-30

30 Tablets

No. 4112

ZyPREXA

Olanzapine
Tablets

LILLY
4112

2.5 mg
Rx only

Medication Guide is to be
dispensed to patients.

CHEPLAPHARM

PRINCIPAL DISPLAY PANEL - 5 mg Tablet Bottle Label

NDC 61269-631-30

30 Tablets

No. 4115

ZyPREXA

Olanzapine
Tablets

LILLY
4115

5 mg
Rx only

Medication Guide is to be
dispensed to patients.

CHEPLAPHARM

PRINCIPAL DISPLAY PANEL - 7.5 mg Tablet Bottle Label

NDC 61269-632-30

30 Tablets

No. 4116

ZyPREXA

Olanzapine
Tablets

LILLY
4116

7.5 mg
Rx only

Medication Guide is to be
dispensed to patients.

CHEPLAPHARM

PRINCIPAL DISPLAY PANEL - 10 mg Tablet Bottle Label

NDC 61269-633-30

30 Tablets

No. 4117

ZyPREXA

Olanzapine
Tablets

LILLY
4117

10 mg
Rx only

Medication Guide is to be
dispensed to patients.

CHEPLAPHARM

PRINCIPAL DISPLAY PANEL - 15 mg Tablet Bottle Label

NDC 61269-634-30

30 Tablets

No. 4415

ZyPREXA

Olanzapine
Tablets

LILLY
4415

15 mg
Rx only

Medication Guide is to be
dispensed to patients.

CHEPLAPHARM

PRINCIPAL DISPLAY PANEL - 20 mg Tablet Bottle Label

NDC 61269-635-30

30 Tablets

No. 4420

ZyPREXA

Olanzapine
Tablets

LILLY
4420

20 mg
Rx only

Medication Guide is to be
dispensed to patients.

CHEPLAPHARM

PRINCIPAL DISPLAY PANEL - 5 mg Tablet Sachet Carton

5 mg orally disintegrating tablets

30 Sachets, No. 4453

NDC 61269-650-35

Rx only

Medication Guide is to
be dispensed to patients.

ZYPrexa®
ZYDIS®

Olanzapine Orally Disintegrating Tablets

5 mg

Phenylketonurics: Contains phenylalanine 0.34 mg per tablet.

DO NOT OPEN POUCH UNTIL IMMEDIATELY PRIOR TO USE.

CHEPLAPHARM

PRINCIPAL DISPLAY PANEL - 10 mg Tablet Sachet Carton

10 mg orally disintegrating tablets

30 Sachets, No. 4454

NDC 61269-651-35

Rx only

Medication Guide is to
be dispensed to patients.

ZYPrexa®
ZYDIS®

Olanzapine Orally Disintegrating Tablets

10 mg

Phenylketonurics: Contains phenylalanine 0.45 mg per tablet.

DO NOT OPEN POUCH UNTIL IMMEDIATELY PRIOR TO USE.

CHEPLAPHARM

PRINCIPAL DISPLAY PANEL - 15 mg Tablet Sachet Carton

15 mg orally disintegrating tablets

30 Sachets, No. 4455

NDC 61269-652-35

Rx only

Medication Guide is to
be dispensed to patients.

ZYPrexa®
ZYDIS®

Olanzapine Orally Disintegrating Tablets

15 mg

Phenylketonurics: Contains phenylalanine 0.67 mg per tablet.

DO NOT OPEN POUCH UNTIL IMMEDIATELY PRIOR TO USE.

CHEPLAPHARM

PRINCIPAL DISPLAY PANEL - 20 mg Tablet Sachet Carton

20 mg orally disintegrating tablets

30 Sachets, No. 4456

NDC 61269-653-35

Rx only

Medication Guide is to
be dispensed to patients.

ZYPrexa®
ZYDIS®

Olanzapine Orally Disintegrating Tablets

20 mg

Phenylketonurics: Contains phenylalanine 0.90 mg per tablet.

DO NOT OPEN POUCH UNTIL IMMEDIATELY PRIOR TO USE.

CHEPLAPHARM

PACKAGE LABEL - ZYPREXA INTRAMUSCULAR 10 mg/vial

NDC 61269-640-20

1 Vial

ZYPREXA® IntraMuscular

Olanzapine for Injection

Sterile Single-Dose Vial

Rx only

For intramuscular use only.

10 mg/vial

CHEPLAPHARM